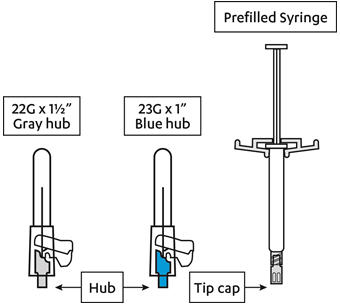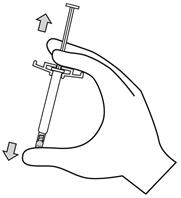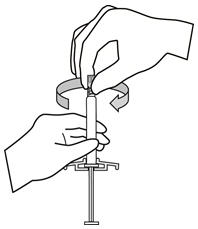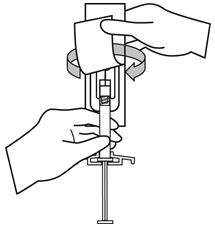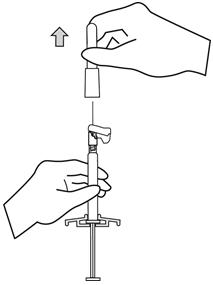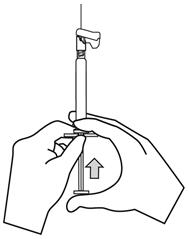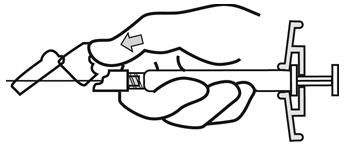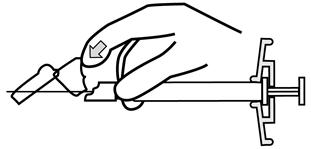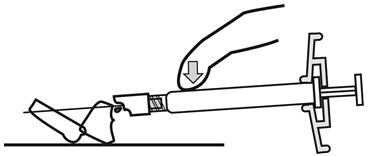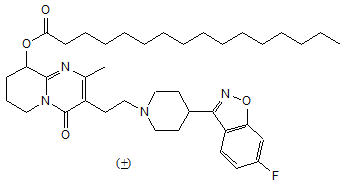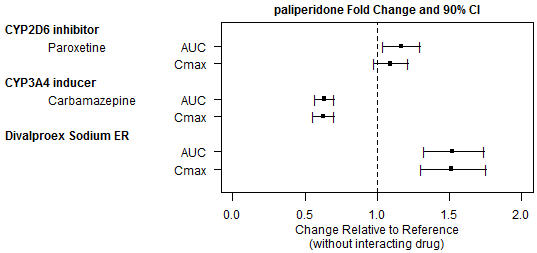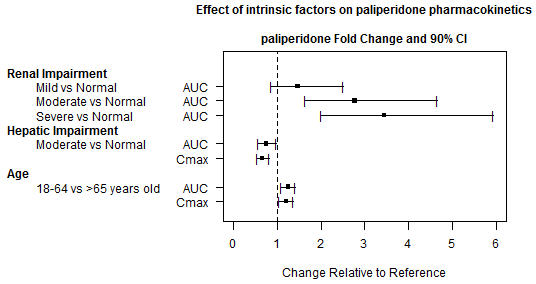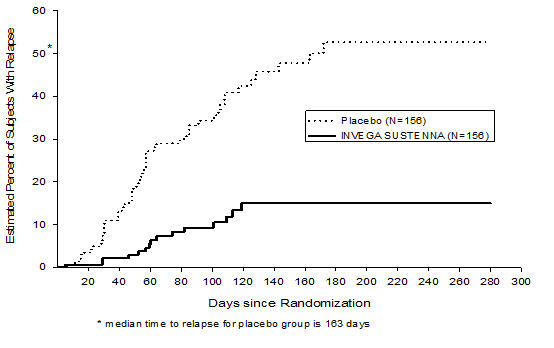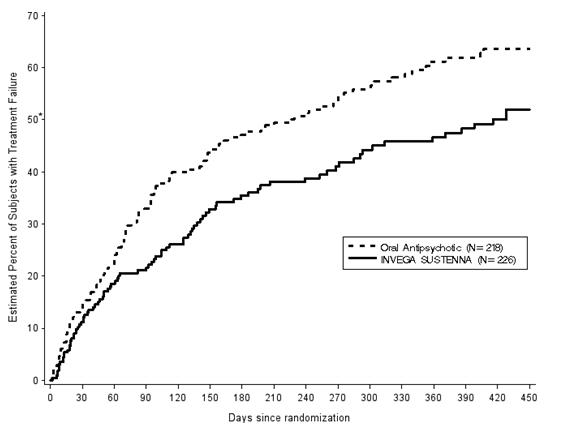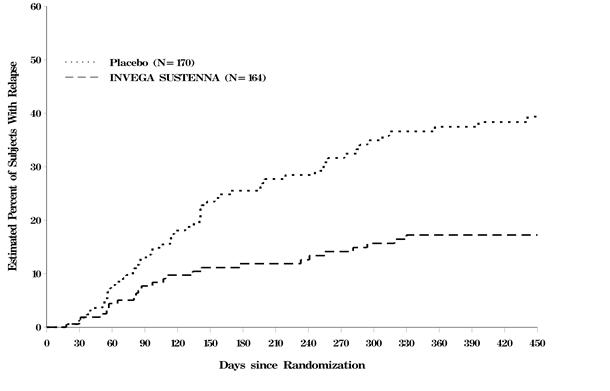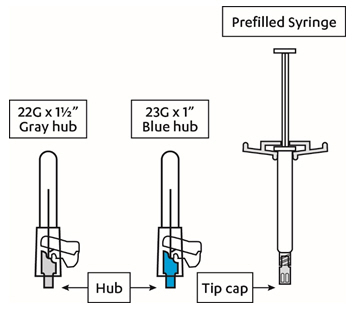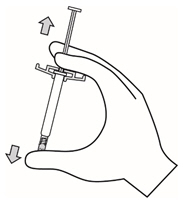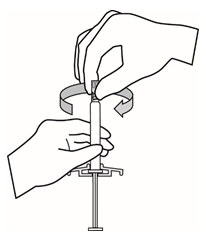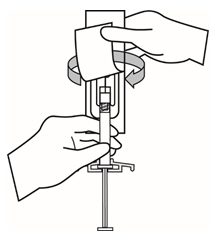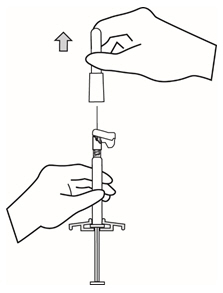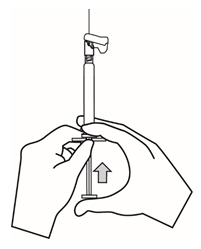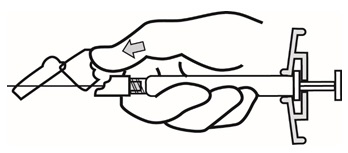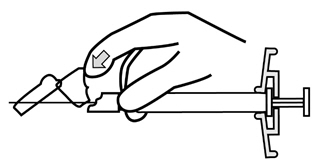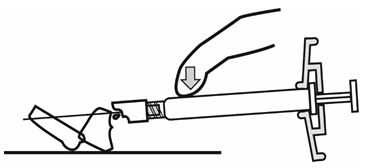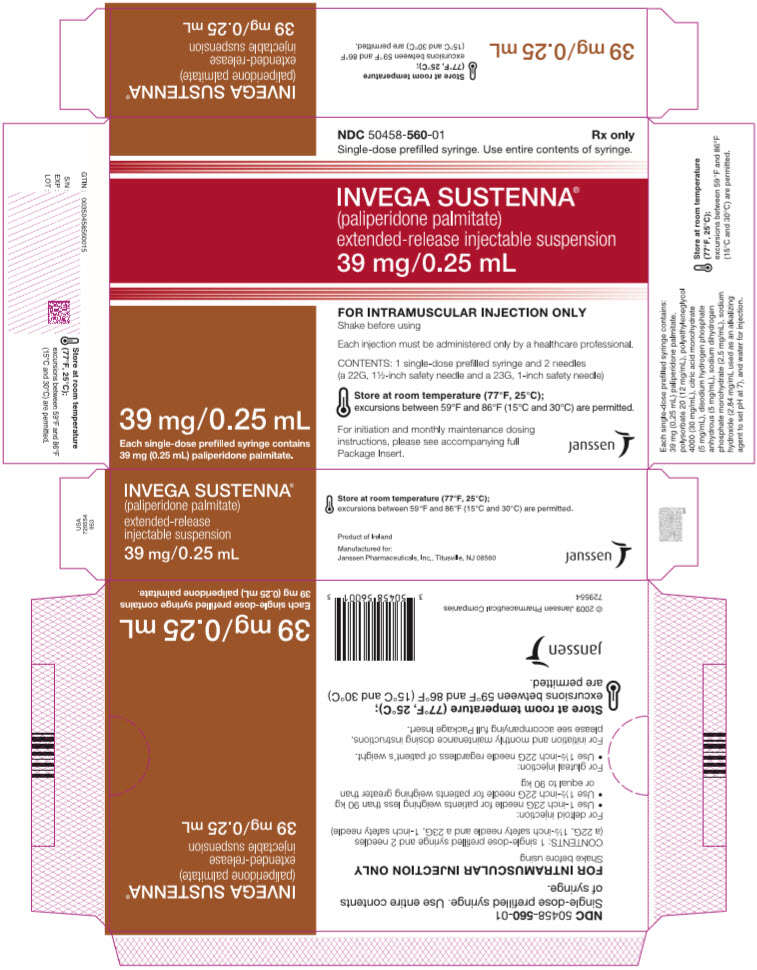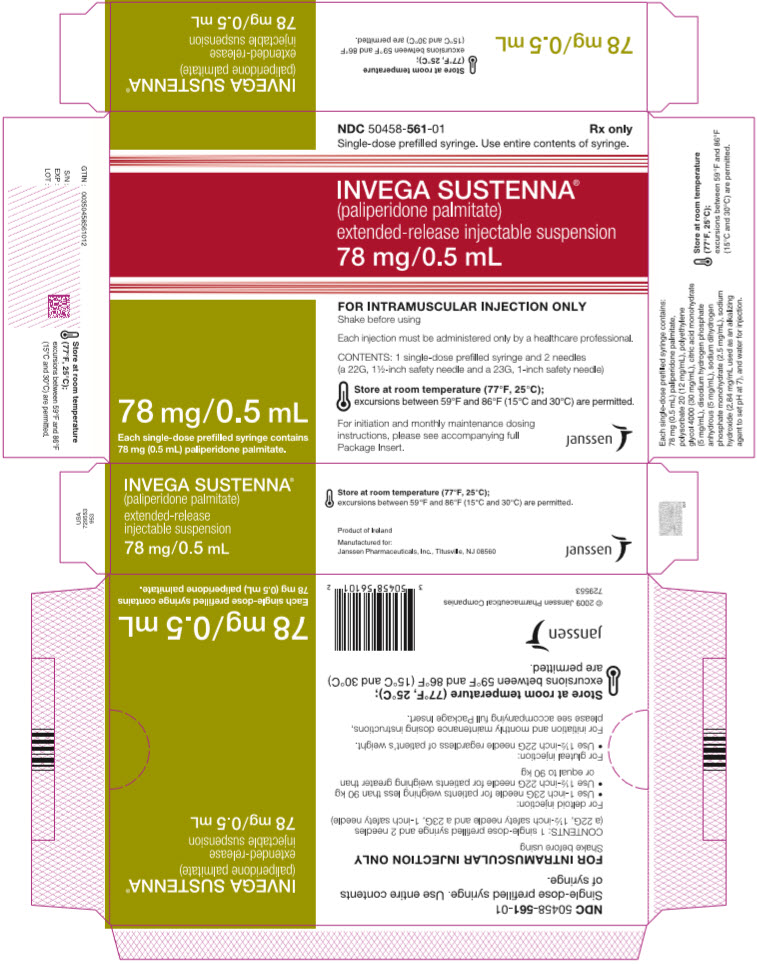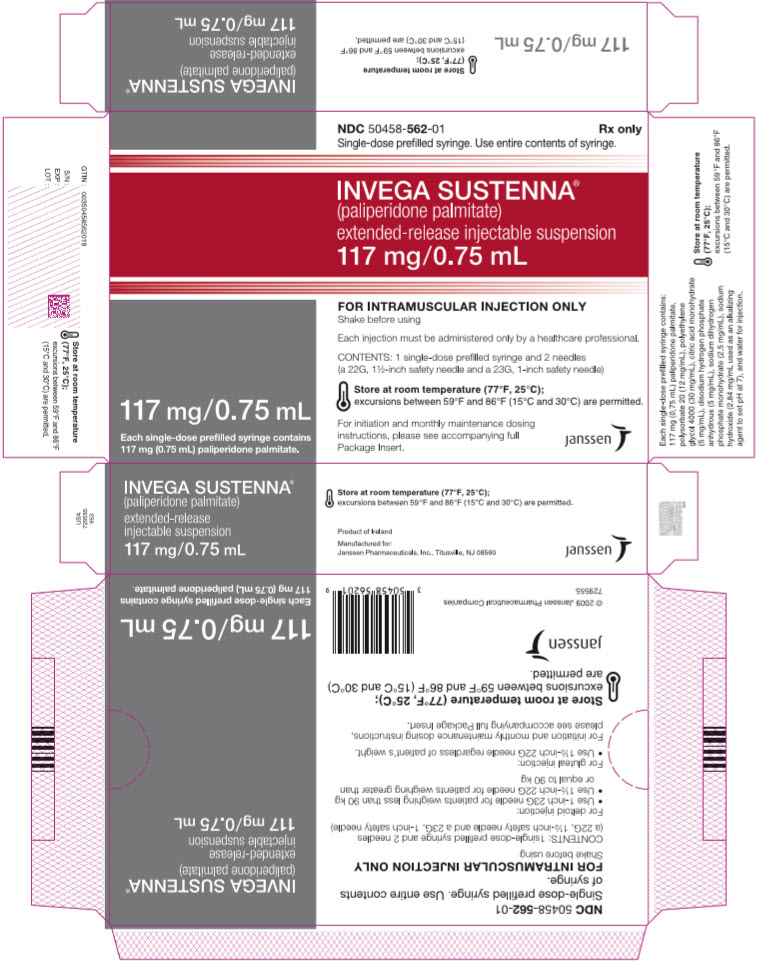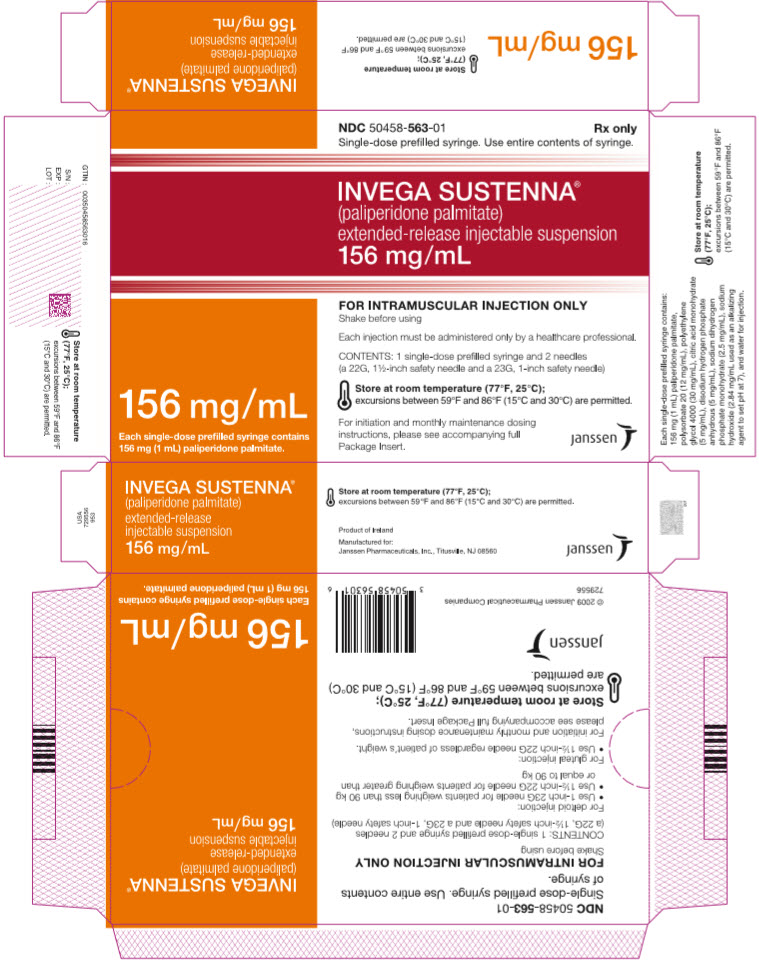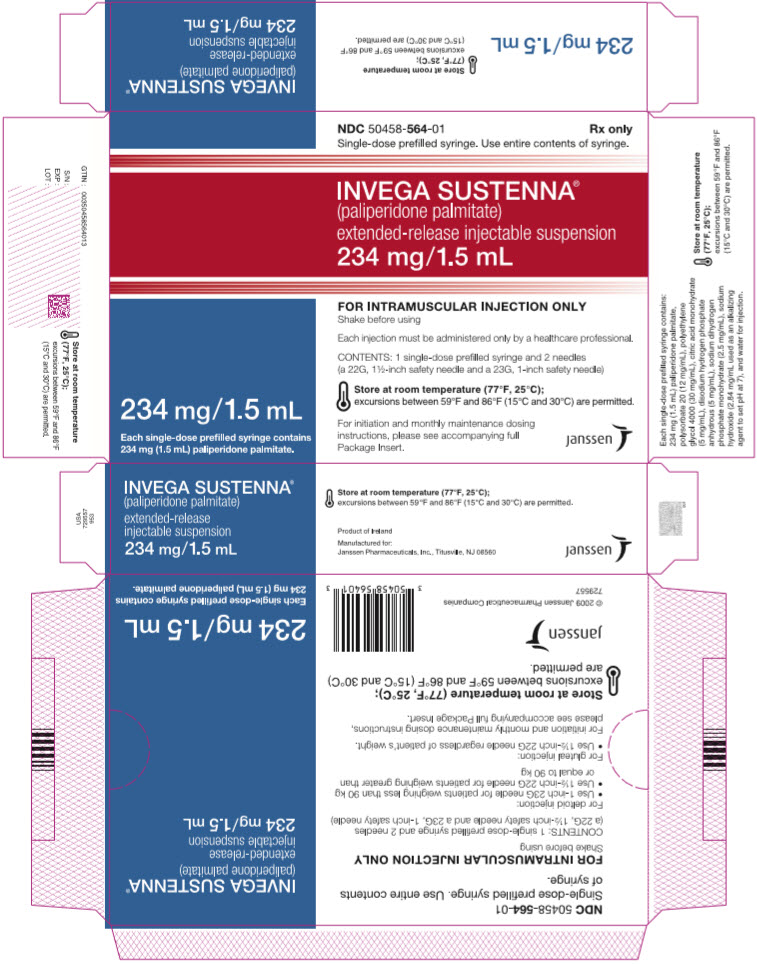 DRUG LABEL: INVEGA SUSTENNA
NDC: 50458-560 | Form: INJECTION
Manufacturer: Janssen Pharmaceuticals, Inc.
Category: prescription | Type: HUMAN PRESCRIPTION DRUG LABEL
Date: 20250214

ACTIVE INGREDIENTS: PALIPERIDONE PALMITATE 39 mg/0.25 mL
INACTIVE INGREDIENTS: POLYSORBATE 20; POLYETHYLENE GLYCOL 4000; CITRIC ACID MONOHYDRATE; SODIUM PHOSPHATE, DIBASIC, ANHYDROUS; SODIUM PHOSPHATE, MONOBASIC, UNSPECIFIED FORM; SODIUM HYDROXIDE; WATER

HIGHLIGHTS OF PRESCRIBING INFORMATION

These highlights do not include all the information needed to use INVEGA SUSTENNA safely and effectively. See full prescribing information for INVEGA SUSTENNA.
INVEGA SUSTENNA® (paliperidone palmitate) extended-release injectable suspension, for intramuscular use
Initial U.S. Approval: 2006

WARNING: INCREASED MORTALITY IN ELDERLY PATIENTS WITH DEMENTIA-RELATED PSYCHOSIS

See full prescribing information for complete boxed warning.

Elderly patients with dementia-related psychosis treated with antipsychotic drugs are at an increased risk of death. INVEGA SUSTENNA is not approved for use in patients with dementia-related psychosis. (5.1)

RECENT MAJOR CHANGES

Dosage and Administration (2.7) | 9/2024
Warnings and Precautions (5.10) | 1/2025

1 INDICATIONS AND USAGE

INVEGA SUSTENNA is an atypical antipsychotic indicated for

- Treatment of schizophrenia in adults. (1)
- Treatment of schizoaffective disorder in adults as monotherapy and as an adjunct to mood stabilizers or antidepressants. (1)

2 DOSAGE AND ADMINISTRATION

- For intramuscular injection only. (2.1)
- Each injection must be administered only by a healthcare professional. (2.1)
- For deltoid injection, use 1-inch 23G needle for patients weighing less than 90 kg or 1½-inch 22G needle for patients weighing 90 kg or more. For gluteal injection, use 1½-inch 22G needle regardless of patient weight. (2.1)

Indication | Initiation Dosing (deltoid) |  | Monthly Maintenance Dose [Administered 5 weeks after the first injection.] (deltoid or gluteal) | Maximum Monthly Dose
Indication | Day 1 | Day 8 | Monthly Maintenance Dose [Administered 5 weeks after the first injection.] (deltoid or gluteal) | Maximum Monthly Dose
Schizophrenia (2.2) | 234 mg | 156 mg | 39–234 mg [The recommended maintenance dose for treatment of schizophrenia is 117 mg. Some patients may benefit from lower or higher maintenance doses within the additional available strengths (39 mg, 78 mg, 156 mg, and 234 mg).] | 234 mg
Schizoaffective disorder (2.2) | 234 mg | 156 mg | 78–234 mg [Adjust dose based on tolerability and/or efficacy using available strengths. The 39 mg strength was not studied in the long-term schizoaffective disorder study.] | 234 mg

- For patients naïve to oral paliperidone or oral or injectable risperidone, establish tolerability with oral paliperidone or oral risperidone prior to initiating treatment with INVEGA SUSTENNA. (2.2)
- Missed Doses: To manage either a missed second initiation dose or a missed monthly maintenance dose, refer to the Full Prescribing Information. (2.3)
- Moderate to severe renal impairment (creatinine clearance < 50 mL/min): INVEGA SUSTENNA is not recommended. (2.5)
- Mild renal impairment (creatinine clearance ≥ 50 mL/min to < 80 mL/min): Administer 156 mg on treatment Day 1 and 117 mg on Day 8, both in the deltoid muscle. Follow with the recommended monthly maintenance dose of 78 mg, administered in the deltoid or gluteal muscle. Adjust monthly maintenance dose based on tolerability and/or efficacy within the strengths of 39 mg, 78 mg, 117 mg, or 156 mg. The maximum monthly dose is 156 mg for patients with mild renal impairment. (2.5)

3 DOSAGE FORMS AND STRENGTHS

Extended-release injectable suspension: 39 mg/0.25 mL, 78 mg/0.5 mL, 117 mg/0.75 mL, 156 mg/mL, or 234 mg/1.5 mL (3)

4 CONTRAINDICATIONS

Known hypersensitivity to paliperidone, risperidone, or to any excipients in INVEGA SUSTENNA. (4)

5 WARNINGS AND PRECAUTIONS

- Cerebrovascular Adverse Reactions, Including Stroke, in Elderly Patients with Dementia-Related Psychosis:Increased incidence of cerebrovascular adverse reactions (e.g. stroke, transient ischemic attack). (5.2)
- Neuroleptic Malignant Syndrome: Manage with immediate discontinuation of drug and close monitoring. (5.3)
- QT Prolongation: Avoid use with drugs that also increase QT interval and in patients with risk factors for prolonged QT interval. (5.4)
- Tardive Dyskinesia: Discontinue drug if clinically appropriate. (5.5)
- Metabolic Changes: Monitor for hyperglycemia/diabetes mellitus, dyslipidemia and weight gain. (5.6)
- Orthostatic Hypotension and Syncope: Monitor heart rate and blood pressure and warn patients with known cardiovascular or cerebrovascular disease, and risk of dehydration or syncope. (5.7)
- Leukopenia, Neutropenia, and Agranulocytosis: Perform complete blood counts (CBC) in patients with pre-existing low white blood cell count (WBC) or history of leukopenia or neutropenia. Consider discontinuing INVEGA SUSTENNA if clinically significant decline in WBC in the absence of other causative factors. (5.9)
- Hyperprolactinemia: Prolactin elevations occur and persist during chronic administration. (5.10)
- Potential for Cognitive and Motor Impairment: Use caution when operating machinery. (5.11)
- Seizures: Use cautiously in patients with a history of seizures or with conditions that lower the seizure threshold. (5.12)

6 ADVERSE REACTIONS

The most common adverse reactions (incidence ≥ 5% and occurring at least twice as often as placebo) were injection site reactions, somnolence/sedation, dizziness, akathisia, and extrapyramidal disorder. (6)

To report SUSPECTED ADVERSE REACTIONS, contact Janssen Pharmaceuticals, Inc. at 1-800-526-7736 or FDA at 1-800-FDA-1088 orwww.fda.gov/medwatch

7 DRUG INTERACTIONS

- Drugs that may cause orthostatic hypotension:An additive effect may occur when co-administered with INVEGA SUSTENNA. (7.1)
- Strong CYP3A4/P-glycoprotein (P-gp) inducers: Avoid using a strong inducer of CYP3A4 and/or P-gp (e.g., carbamazepine, rifampin, St John's Wort) during a dosing interval for INVEGA SUSTENNA. If administering a strong inducer is necessary, consider managing the patient using paliperidone extended-release tablets. (2.5, 7.1, 12.3)

8 USE IN SPECIFIC POPULATIONS

Pregnancy: May cause extrapyramidal and/or withdrawal symptoms in neonates with third trimester exposure. (8.1)

FULL PRESCRIBING INFORMATION

WARNING: INCREASED MORTALITY IN ELDERLY PATIENTS WITH DEMENTIA-RELATED PSYCHOSIS

Elderly patients with dementia-related psychosis treated with antipsychotic drugs are at an increased risk of death. INVEGA SUSTENNA is not approved for use in patients with dementia-related psychosis. [see Warnings and Precautions (5.1)] .

1 INDICATIONS AND USAGE

INVEGA SUSTENNA (paliperidone palmitate) is indicated for the treatment of:

- Schizophrenia in adults [see Clinical Studies (14.1)].
- Schizoaffective disorder in adults as monotherapy and as an adjunct to mood stabilizers or antidepressants [see Clinical Studies (14.2)].

2 DOSAGE AND ADMINISTRATION

2.1 Administration Instructions

Each injection must be administered only by a healthcare professional.

Parenteral drug products should be inspected visually for foreign matter and discoloration prior to administration, whenever product and container permit.

INVEGA SUSTENNA is intended for intramuscular use only. Do not administer by any other route. Avoid inadvertent injection into a blood vessel. Administer the dose in a single injection; do not administer the dose in divided injections. Inject slowly, deep into the deltoid or gluteal muscle.

INVEGA SUSTENNA must be administered using only the needles that are provided in the INVEGA SUSTENNA kit.

The recommended needle size for administration of INVEGA SUSTENNA into the deltoid muscle is determined by the patient's weight:

- For patients weighing less than 90 kg, the 1-inch, 23 gauge needle is recommended.
- For patients weighing 90 kg or more, the 1½-inch, 22 gauge needle is recommended.

Deltoid injections should be alternated between the two deltoid muscles.

The recommended needle size for administration of INVEGA SUSTENNA into the gluteal muscle is the 1½-inch, 22 gauge needle regardless of patient weight.

Administer into the upper-outer quadrant of the gluteal muscle. Gluteal injections should be alternated between the two gluteal muscles.

2.2 Schizophrenia and Schizoaffective Disorder

For patients who have never taken oral paliperidone or oral or injectable risperidone, it is recommended to establish tolerability with oral paliperidone or oral risperidone prior to initiating treatment with INVEGA SUSTENNA.

The recommended dosing of INVEGA SUSTENNA for each approved indication is displayed in Table 1. The recommended initiation of INVEGA SUSTENNA is with a dose of 234 mg on treatment day 1 and 156 mg one week later, both administered in the deltoid muscle. Following the second initiation dose, monthly maintenance doses can be administered in either the deltoid or gluteal muscle.

Table 1: Recommended Dosing of INVEGA SUSTENNA for Adults with Schizophrenia or Schizoaffective Disorder
Indication | Initiation Dosing (deltoid) |  | Monthly Maintenance Dose [Administered 5 weeks after the first injection.] (deltoid or gluteal) | Maximum Monthly Dose
Indication | Day 1 | Day 8 | Monthly Maintenance Dose [Administered 5 weeks after the first injection.] (deltoid or gluteal) | Maximum Monthly Dose
Schizophrenia | 234 mg | 156 mg | 39–234 mg [The recommended maintenance dose for treatment of schizophrenia is 117 mg. Some patients may benefit from lower or higher maintenance doses within the additional available strengths (39 mg, 78 mg, 156 mg, and 234 mg).] | 234 mg
Schizoaffective disorder | 234 mg | 156 mg | 78–234 mg [Adjust dose based on tolerability and/or efficacy using available strengths. The 39 mg strength was not studied in the long-term schizoaffective disorder study.] | 234 mg

Adjustment of the maintenance dose may be made monthly. When making dose adjustments, the prolonged-release characteristics of INVEGA SUSTENNA should be considered [see Clinical Pharmacology (12.3)] , as the full effect of the dose adjustment may not be evident for several months.

2.3 Missed Doses

Avoiding Missed Doses

It is recommended that the second initiation dose of INVEGA SUSTENNA be given one week after the first dose. To avoid a missed dose, patients may be given the second dose 4 days before or after the one-week time point. Similarly, the third and subsequent injections after the initiation regimen are recommended to be given monthly. To avoid a missed monthly dose, patients may be given the injection up to 7 days before or after the monthly time point.

Management of a Missed Second Initiation Dose

If the target date for the second INVEGA SUSTENNA injection (one week ± 4 days) is missed, the recommended reinitiation depends on the length of time which has elapsed since the patient's first injection. In case of a missed second initiation dose follow the dosing instructions provided in Table 2.

Table 2: Management of a Missed Second Initiation Dose
TIMING OF MISSED SECOND INITIATION DOSE | DOSING
Less than 4 weeks since first injection | Administer the second initiation dose of 156 mg in the deltoid muscle as soon as possible.; 1. It is recommended to administer a third injection of 117 mg in either the deltoid or gluteal muscle 5 weeks after the first injection (regardless of the timing of the second injection). 2. Thereafter, resume regular monthly dosing in either the deltoid or gluteal muscle.
4 to 7 weeks since first injection | Resume dosing with two injections of 156 mg in the following manner:; 1. Administer a deltoid injection as soon as possible. 2. Administer a second deltoid injection 1 week later. 3. Thereafter, resume regular monthly dosing in either the deltoid or gluteal muscle.
More than 7 weeks since first injection | Restart dosing with recommended initiation (see Section 2.2, Table 1) :; 1. Administer a 234 mg deltoid injection on Day 1. 2. Administer a 156 mg deltoid injection 1 week later. 3. Thereafter, resume regular monthly dosing in either the deltoid or gluteal muscle.

Management of a Missed Maintenance Dose

In case of a missed maintenance dose follow the dosing instructions provided in Table 3.

Table 3: Management of a Missed Maintenance Dose
TIMING OF MISSED MAINTENANCE DOSE | DOSING
4 to 6 weeks since last injection | Resume regular monthly dosing as soon as possible at the patient's previously stabilized dose, followed by injections at monthly intervals.
More than 6 weeks to 6 months since last injection | Resume the same dose the patient was previously stabilized on (unless the patient was stabilized on a dose of 234 mg, then the first 2 injections should each be 156 mg) in the following manner:; 1. Administer a deltoid injection as soon as possible. 2. Administer a second deltoid injection 1 week later at the same dose. 3. Thereafter, resume administering the previously stabilized dose in the deltoid or gluteal muscle 1 month after the second injection.
More than 6 months since last injection | Restart dosing with recommended initiation(see Section 2.2, Table 1) :; 1. Administer a 234 mg deltoid injection on Day 1. 2. Administer a 156 mg deltoid injection 1 week later. 3. Thereafter, resume administering the previously stabilized dose in the deltoid or gluteal muscle 1 month after the second injection.

2.4 Use with Risperidone or with Oral Paliperidone

Since paliperidone is the major active metabolite of risperidone, caution should be exercised when INVEGA SUSTENNA is coadministered with risperidone or with oral paliperidone for extended periods of time. Safety data involving concomitant use of INVEGA SUSTENNA with other antipsychotics is limited.

2.5 Dosage Adjustments

Patients with Renal Impairment

INVEGA SUSTENNA has not been systematically studied in patients with renal impairment [see Clinical Pharmacology (12.3)] .

For patients with mild renal impairment (creatinine clearance ≥ 50 mL/min to < 80 mL/min [Cockcroft-Gault Formula]), initiate INVEGA SUSTENNA with a dose of 156 mg on treatment Day 1 and 117 mg on Day 8, both in the deltoid muscle. Follow with the recommended monthly maintenance dose of 78 mg, administered in either the deltoid or gluteal muscle. Adjust monthly maintenance dose based on tolerability and/or efficacy within the strengths of 39 mg, 78 mg, 117 mg, or 156 mg. The maximum monthly dose is 156 mg for patients with mild renal impairment [see Use in Specific Populations (8.6) and Clinical Pharmacology (12.3)] .

INVEGA SUSTENNA is not recommended in patients with moderate or severe renal impairment (creatinine clearance < 50 mL/min) [see Use in Specific Populations (8.6) and Clinical Pharmacology (12.3)] .

Coadministration with Strong CYP3A4/P-glycoprotein (P-gp) Inducers

Avoid using a strong inducer of CYP3A4 and/or P-gp (e.g., carbamazepine, rifampin, St John's Wort) during the 1-month dosing interval for INVEGA SUSTENNA, if possible. If administering a strong inducer is necessary, consider managing the patient using paliperidone extended release tablets [see Drug Interactions (7.1) and Clinical Pharmacology (12.3)] .

2.6 Switching from Other Antipsychotics

There are no systematically collected data to specifically address switching patients with schizophrenia or schizoaffective disorder from other antipsychotics to INVEGA SUSTENNA, or concerning concomitant administration with other antipsychotics.

Switching from Oral Antipsychotics

For patients who have never taken oral paliperidone or oral or injectable risperidone, tolerability should be established with oral paliperidone or oral risperidone prior to initiating treatment with INVEGA SUSTENNA.

Previous oral antipsychotics can be gradually discontinued at the time of initiation of treatment with INVEGA SUSTENNA. Recommended initiation of INVEGA SUSTENNA is with a dose of 234 mg on treatment day 1 and 156 mg one week later, both administered in the deltoid muscle [see Dosage and Administration (2.2)] . Patients previously stabilized on different doses of INVEGA Extended-Release tablets can attain similar paliperidone steady-state exposure during maintenance treatment with INVEGA SUSTENNA monthly doses as depicted in Table 4.

Table 4: Doses of INVEGA and INVEGA SUSTENNA Needed to Attain Similar Steady-State Paliperidone Exposure During Maintenance Treatment
Formulation | INVEGA Extended-Release Tablet | INVEGA SUSTENNA Injection
Dosing Frequency | Once Daily | Once every 4 weeks
Dose (mg) | 12 | 234
Dose (mg) | 9 | 156
Dose (mg) | 6 | 117
Dose (mg) | 3 | 39–78

Switching from Long-Acting Injectable Antipsychotics

For patients who have never taken oral paliperidone or oral or injectable risperidone, tolerability should be established with oral paliperidone or oral risperidone prior to initiating treatment with INVEGA SUSTENNA.

When switching patients currently at steady-state on a long-acting injectable antipsychotic, initiate INVEGA SUSTENNA therapy in place of the next scheduled injection. INVEGA SUSTENNA should then be continued at monthly intervals. The one-week initiation dosing regimen as described in Section 2.2 is not required. See Table 1 above for recommended monthly maintenance dosing. Based on previous clinical history of tolerability and/or efficacy, some patients may benefit from lower or higher maintenance doses within the available strengths (39 mg, 78 mg, 117 mg, 156 mg, and 234 mg). The 39 mg strength was not studied in the long-term schizoaffective disorder study. Monthly maintenance doses can be administered in either the deltoid or gluteal muscle [see Dosage and Administration (2.2)] .

If INVEGA SUSTENNA is discontinued, its prolonged-release characteristics must be considered. As recommended with other antipsychotic medications, the need for continuing existing extrapyramidal symptoms (EPS) medication should be re-evaluated periodically.

2.7 Instructions for Preparation and Administration

Each injection must be administered only by a healthcare professional.

The kit contains a prefilled syringe and 2 safety needles (a 1 ½-inch 22 gauge needle and a 1-inch 23 gauge needle) for intramuscular injection.

INVEGA SUSTENNA is for single use only.

- Shake the syringe vigorously for a minimum of 10 seconds to ensure a homogeneous suspension.
- Select the appropriate needle.
  For DELTOID injection:
  - If the patient weighs less than 90 kg, use the 1-inch 23 gauge needle (needle with blue colored hub).
  - If the patient weighs 90 kg or more, use the 1 ½-inch 22 gauge needle (needle with gray colored hub).
  For GLUTEAL injection:
  Use the 1 ½-inch 22 gauge needle (needle with gray colored hub) regardless of patient's weight.
- Hold the syringe with the tip cap pointing up. Remove the rubber tip cap with a gentle twisting motion.
- Peel the safety needle pouch half way open. Grasp the needle sheath using the plastic peel pouch. Hold the syringe pointing up. Attach the safety needle to the syringe using a gentle twisting motion to avoid needle hub cracks or damage. Always check for signs of damage or leaking prior to administration.
- Pull the needle sheath away from the needle with a straight pull. Do not twist the sheath as the needle may be loosened from the syringe.
- Bring the syringe with the attached needle in upright position to de-aerate. De-aerate the syringe by moving the plunger rod carefully forward.
- Inject the entire contents intramuscularly slowly, deep into the selected deltoid or gluteal muscle of the patient. Do not administer by any other route.
- After the injection is complete, use either thumb or finger of one hand (h1, h2) or a flat surface (h3) to activate the needle protection system. The needle protection system is fully activated when a 'click' is heard. Discard the syringe with needle appropriately.

h1

h2

h3

3 DOSAGE FORMS AND STRENGTHS

INVEGA SUSTENNA is available as a white to off-white aqueous extended-release injectable suspension for intramuscular injection in dose strengths of 39 mg/0.25 mL, 78 mg/0.5 mL, 117 mg/0.75 mL, 156 mg/mL, and 234 mg/1.5 mL paliperidone palmitate in single-dose prefilled syringes.

4 CONTRAINDICATIONS

INVEGA SUSTENNA is contraindicated in patients with a known hypersensitivity to either paliperidone or risperidone, or to any of the excipients in the INVEGA SUSTENNA formulation. Hypersensitivity reactions, including anaphylactic reactions and angioedema, have been reported in patients treated with risperidone and in patients treated with paliperidone. Paliperidone palmitate is converted to paliperidone, which is a metabolite of risperidone.

5 WARNINGS AND PRECAUTIONS

5.1 Increased Mortality in Elderly Patients with Dementia-Related Psychosis

Elderly patients with dementia-related psychosis treated with antipsychotic drugs are at an increased risk of death. Analyses of 17 placebo-controlled trials (modal duration of 10 weeks), largely in patients taking atypical antipsychotic drugs, revealed a risk of death in drug-treated patients of between 1.6 to 1.7 times the risk of death in placebo-treated patients. Over the course of a typical 10-week controlled trial, the rate of death in drug-treated patients was about 4.5%, compared to a rate of about 2.6% in the placebo group. Although the causes of death were varied, most of the deaths appeared to be either cardiovascular (e.g., heart failure, sudden death) or infectious (e.g., pneumonia) in nature. Observational studies suggest that, similar to atypical antipsychotic drugs, treatment with conventional antipsychotic drugs may increase mortality. The extent to which the findings of increased mortality in observational studies may be attributed to the antipsychotic drug as opposed to some characteristic(s) of the patients is not clear. INVEGA SUSTENNA is not approved for the treatment of patients with dementia-related psychosis [see Boxed Warning and Warnings and Precautions (5.2)] .

5.2 Cerebrovascular Adverse Reactions, Including Stroke, in Elderly Patients with Dementia-Related Psychosis

In placebo-controlled trials with risperidone, aripiprazole, and olanzapine in elderly subjects with dementia, there was a higher incidence of cerebrovascular adverse reactions (cerebrovascular accidents and transient ischemic attacks) including fatalities compared to placebo-treated subjects. No studies have been conducted with oral paliperidone, INVEGA SUSTENNA, or the 3-month paliperidone palmitate extended-release injectable suspension in elderly patients with dementia. These medicines are not approved for the treatment of patients with dementia-related psychosis [see Boxed Warning and Warnings and Precautions (5.1)] .

5.3 Neuroleptic Malignant Syndrome

Neuroleptic Malignant Syndrome (NMS), a potentially fatal symptom complex, has been reported in association with antipsychotic drugs, including paliperidone.

Clinical manifestations of NMS are hyperpyrexia, muscle rigidity, altered mental status including delirium, and autonomic instability (irregular pulse or blood pressure, tachycardia, diaphoresis, and cardiac dysrhythmia). Additional signs may include elevated creatine phosphokinase, myoglobinuria (rhabdomyolysis), and acute renal failure.

If NMS is suspected, immediately discontinue INVEGA SUSTENNA and provide symptomatic treatment and monitoring.

5.4 QT Prolongation

Paliperidone causes a modest increase in the corrected QT (QTc) interval. The use of paliperidone should be avoided in combination with other drugs that are known to prolong QTc including Class 1A (e.g., quinidine, procainamide) or Class III (e.g., amiodarone, sotalol) antiarrhythmic medications, antipsychotic medications (e.g., chlorpromazine, thioridazine), antibiotics (e.g., gatifloxacin, moxifloxacin), or any other class of medications known to prolong the QTc interval. Paliperidone should also be avoided in patients with congenital long QT syndrome and in patients with a history of cardiac arrhythmias.

Certain circumstances may increase the risk of the occurrence of Torsades de pointes and/or sudden death in association with the use of drugs that prolong the QTc interval, including (1) bradycardia; (2) hypokalemia or hypomagnesemia; (3) concomitant use of other drugs that prolong the QTc interval; and (4) presence of congenital prolongation of the QT interval.

The effects of oral paliperidone on the QT interval were evaluated in a double-blind, active-controlled (moxifloxacin 400 mg single dose), multicenter QT study in adults with schizophrenia and schizoaffective disorder, and in three placebo- and active-controlled 6-week, fixed-dose efficacy trials in adults with schizophrenia.

In the QT study (n=141), the 8 mg dose of immediate-release oral paliperidone (n=50) showed a mean placebo-subtracted increase from baseline in QTcLD of 12.3 msec (90% CI: 8.9; 15.6) on day 8 at 1.5 hours post-dose. The mean steady-state peak plasma concentration for this 8 mg dose of paliperidone immediate release (Cmax ss = 113 ng/mL) was more than 2-fold the exposure observed with the maximum recommended 234 mg dose of INVEGA SUSTENNA administered in the deltoid muscle (predicted median Cmax ss = 50 ng/mL). In this same study, a 4 mg dose of the immediate-release oral formulation of paliperidone, for which Cmax ss = 35 ng/mL, showed an increased placebo-subtracted QTcLD of 6.8 msec (90% CI: 3.6; 10.1) on day 2 at 1.5 hours post-dose.

In the three fixed-dose efficacy studies of oral paliperidone extended release in subjects with schizophrenia, electrocardiogram (ECG) measurements taken at various time points showed only one subject in the oral paliperidone 12 mg group had a change exceeding 60 msec at one time-point on Day 6 (increase of 62 msec).

In the four fixed-dose efficacy studies of INVEGA SUSTENNA in subjects with schizophrenia and in the long-term study in subjects with schizoaffective disorder, no subject experienced a change in QTcLD exceeding 60 msec and no subject had a QTcLD value of > 500 msec at any time point. In the maintenance study in subjects with schizophrenia, no subject had a QTcLD change > 60 msec, and one subject had a QTcLD value of 507 msec (Bazett's QT corrected interval [QTcB] value of 483 msec); this latter subject also had a heart rate of 45 beats per minute.

5.5 Tardive Dyskinesia

Tardive dyskinesia, a syndrome consisting of potentially irreversible, involuntary, dyskinetic movements, may develop in patients treated with antipsychotic drugs. Although the prevalence of the syndrome appears to be highest among the elderly, especially elderly women, it is impossible to predict which patients will develop the syndrome. Whether antipsychotic drug products differ in their potential to cause tardive dyskinesia is unknown.

The risk of developing tardive dyskinesia and the likelihood that it will become irreversible appear to increase with the duration of treatment and the cumulative dose. The syndrome can develop after relatively brief treatment periods, even at low doses. It may also occur after discontinuation of treatment.

Tardive dyskinesia may remit, partially or completely, if antipsychotic treatment is discontinued. Antipsychotic treatment, itself, however, may suppress (or partially suppress) the signs and symptoms of the syndrome, possibly masking the underlying process. The effect that symptomatic suppression has upon the long-term course of the syndrome is unknown.

Given these considerations, INVEGA SUSTENNA should be prescribed in a manner that is most likely to minimize the occurrence of tardive dyskinesia. Chronic antipsychotic treatment should generally be reserved for patients: (1) who suffer from a chronic illness that is known to respond to antipsychotic drugs, and (2) for whom alternative, equally effective, but potentially less harmful treatments are not available or appropriate. In patients who do require chronic treatment, use the lowest dose and the shortest duration of treatment producing a satisfactory clinical response. Periodically reassess the need for continued treatment.

If signs and symptoms of tardive dyskinesia appear in a patient on INVEGA SUSTENNA, drug discontinuation should be considered. However, some patients may require treatment with INVEGA SUSTENNA despite the presence of the syndrome.

5.6 Metabolic Changes

Atypical antipsychotic drugs have been associated with metabolic changes that may increase cardiovascular/cerebrovascular risk. These metabolic changes include hyperglycemia, dyslipidemia, and body weight gain. While all of the drugs in the class have been shown to produce some metabolic changes, each drug has its own specific risk profile.

Hyperglycemia and Diabetes Mellitus

Hyperglycemia and diabetes mellitus, in some cases extreme and associated with ketoacidosis or hyperosmolar coma or death, have been reported in patients treated with all atypical antipsychotics. These cases were, for the most part, seen in post-marketing clinical use and epidemiologic studies, not in clinical trials. Hyperglycemia and diabetes have been reported in trial subjects treated with INVEGA SUSTENNA. Assessment of the relationship between atypical antipsychotic use and glucose abnormalities is complicated by the possibility of an increased background risk of diabetes mellitus in patients with schizophrenia and the increasing incidence of diabetes mellitus in the general population. Given these confounders, the relationship between atypical antipsychotic use and hyperglycemia-related adverse events is not completely understood. However, epidemiological studies suggest an increased risk of hyperglycemia-related adverse reactions in patients treated with the atypical antipsychotics.

Patients with an established diagnosis of diabetes mellitus who are started on atypical antipsychotics should be monitored regularly for worsening of glucose control. Patients with risk factors for diabetes mellitus (e.g., obesity, family history of diabetes) who are starting treatment with atypical antipsychotics should undergo fasting blood glucose testing at the beginning of treatment and periodically during treatment. Any patient treated with atypical antipsychotics should be monitored for symptoms of hyperglycemia including polydipsia, polyuria, polyphagia, and weakness. Patients who develop symptoms of hyperglycemia during treatment with atypical antipsychotics should undergo fasting blood glucose testing. In some cases, hyperglycemia has resolved when the atypical antipsychotic was discontinued; however, some patients required continuation of anti-diabetic treatment despite discontinuation of the suspect drug.

Pooled data from the four placebo-controlled (one 9-week and three 13-week), fixed-dose studies in subjects with schizophrenia are presented in Table 5.

Table 5: Change in Fasting Glucose from Four Placebo-Controlled, 9- to 13-Week, Fixed-Dose Studies in Subjects with Schizophrenia
 |  | INVEGA SUSTENNA
 | Placebo | 39 mg | 78 mg | 156 mg | 234/39 mg [Initial deltoid injection of 234 mg followed by either 39 mg, 156 mg, or 234 mg every 4 weeks by deltoid or gluteal injection. Other dose groups (39 mg, 78 mg, and 156 mg) are from studies involving only gluteal injection. [see Clinical Studies (14.1)] .] | 234/156 mg | 234/234 mg
 | Mean change from baseline (mg/dL)
 | n=367 | n=86 | n=244 | n=238 | n=110 | n=126 | n=115
Serum Glucose Change from baseline | -1.3 | 1.3 | 3.5 | 0.1 | 3.4 | 1.8 | -0.2
 | Proportion of Patients with Shifts
Serum Glucose Normal to High | 4.6% | 6.3% | 6.4% | 3.9% | 2.5% | 7.0% | 6.6%
(<100 mg/dL to ≥126 mg/dL) | (11/241) | (4/64) | (11/173) | (6/154) | (2/79) | (6/86) | (5/76)

In a long-term open-label pharmacokinetic and safety study in subjects with schizophrenia in which the highest dose available (234 mg) was evaluated, INVEGA SUSTENNA was associated with a mean change in glucose of -0.4 mg/dL at Week 29 (n=109) and +6.8 mg/dL at Week 53 (n=100).

During the initial 25-week open-label period of a long-term study in subjects with schizoaffective disorder, INVEGA SUSTENNA was associated with mean change in glucose of +5.3 mg/dL (n=518). At the endpoint of the subsequent 15-month double-blind period of the study, INVEGA SUSTENNA was associated with a mean change in glucose of +0.3 mg/dL (n=131) compared with a mean change of +4.0 mg/dL in the placebo group (n=120).

Dyslipidemia

Undesirable alterations in lipids have been observed in patients treated with atypical antipsychotics.

Pooled data from the four placebo-controlled (one 9-week and three 13-week), fixed-dose studies in subjects with schizophrenia are presented in Table 6.

Table 6: Change in Fasting Lipids from Four Placebo-Controlled, 9- to 13-Week, Fixed-Dose Studies in Subjects with Schizophrenia
 |  | INVEGA SUSTENNA
 | Placebo | 39 mg | 78 mg | 156 mg | 234/39 mg [Initial deltoid injection of 234 mg followed by either 39 mg, 156 mg, or 234 mg every 4 weeks by deltoid or gluteal injection. Other dose groups (39 mg, 78 mg, and 156 mg) are from studies involving only gluteal injection. [see Clinical Studies (14.1)] .] | 234/156 mg | 234/234 mg
 | Mean change from baseline (mg/dL)
Cholesterol | n=366 | n=89 | n=244 | n=232 | n=105 | n=119 | n=120
Change from baseline | -6.6 | -6.4 | -5.8 | -7.1 | -0.9 | -4.2 | 9.4
LDL | n=275 | n=80 | n=164 | n=141 | n=104 | n=117 | n=108
Change from baseline | -6.0 | -4.8 | -5.6 | -4.8 | 0.9 | -2.4 | 5.2
HDL | n=286 | n=89 | n=165 | n=150 | n=105 | n=118 | n=115
Change from baseline | 0.7 | 2.1 | 0.6 | 0.3 | 1.5 | 1.1 | 0.0
Triglycerides | n=366 | n=89 | n=244 | n=232 | n=105 | n=119 | n=120
Change from baseline | -16.7 | 7.6 | -9.0 | -11.5 | -14.1 | -20.0 | 11.9
 | Proportion of Patients with Shifts
Cholesterol
Normal to High | 3.2% | 2.0% | 2.0% | 2.1% | 0% | 3.1% | 7.1%
(<200 mg/dL to ≥240 mg/dL) | (7/222) | (1/51) | (3/147) | (3/141) | (0/69) | (2/65) | (6/84)
LDL
Normal to High | 1.1% | 0% | 0% | 0% | 0% | 0% | 0%
(<100 mg/dL to ≥160 mg/dL) | (1/95) | (0/29) | (0/67) | (0/46) | (0/41) | (0/37) | (0/44)
HDL
Normal to Low | 13.8% | 14.8% | 9.6% | 14.2% | 12.7% | 10.5% | 16.0%
(≥40 mg/dL to <40 mg/dL) | (28/203) | (9/61) | (11/115) | (15/106) | (9/71) | (8/76) | (13/81)
Triglycerides
Normal to High | 3.6% | 6.1% | 9.2% | 7.2% | 1.3% | 3.7% | 10.7%
(<150 mg/dL to ≥200 mg/dL) | (8/221) | (3/49) | (14/153) | (10/139) | (1/79) | (3/82) | (9/84)

In a long-term open-label pharmacokinetic and safety study in subjects with schizophrenia in which the highest dose available (234 mg) was evaluated, the mean changes from baseline in lipid values are presented in Table 7.

Table 7: Change in Fasting Lipids from Long-term Open-label Pharmacokinetic and Safety Study in Subjects with Schizophrenia
 | INVEGA SUSTENNA 234 mg
 | Week 29 | Week 53
 | Mean change from baseline (mg/dL)
Cholesterol | n=112 | n=100
Change from baseline | -1.2 | 0.1
LDL | n=107 | n=89
Change from baseline | -2.7 | -2.3
HDL | n=112 | n=98
Change from baseline | -0.8 | -2.6
Triglycerides | n=112 | n=100
Change from baseline | 16.2 | 37.4

The mean changes from baseline in lipid values during the initial 25-week open-label period and at the endpoint of the subsequent 15-month double-blind period in a long-term study in subjects with schizoaffective disorder are presented in Table 8.

Table 8: Change in Fasting Lipids from an Open-Label and Double-Blind Periods of a Long-Term Study in Subjects with Schizoaffective Disorder
 | Open-Label Period | Double-Blind Period
 | INVEGA SUSTENNA | Placebo | INVEGA SUSTENNA
 | Mean change from baseline (mg/dL)
Cholesterol | n=198 | n=119 | n=132
Change from baseline | -3.9 | -4.2 | 2.3
LDL | n=198 | n=117 | n=130
Change from baseline | -2.7 | -2.8 | 5.9
HDL | n=198 | n=119 | n=131
Change from baseline | -2.7 | -0.9 | -0.7
Triglycerides | n=198 | n=119 | n=132
Change from baseline | 7.0 | 2.5 | -12.3

Weight Gain

Weight gain has been observed with atypical antipsychotic use. Clinical monitoring of weight is recommended.

Data on mean changes in body weight and the proportion of subjects meeting a weight gain criterion of ≥ 7% of body weight from the four placebo-controlled (one 9-week and three 13-week), fixed-dose studies in subjects with schizophrenia are presented in Table 9.

Table 9: Mean Change in Body Weight (kg) and the Proportion of Subjects with ≥ 7% Gain in Body Weight from Four Placebo-Controlled, 9- to 13-Week, Fixed-Dose Studies in Subjects with Schizophrenia
 |  | INVEGA SUSTENNA
 | Placebo | 39 mg | 78 mg | 156 mg | 234/39 mg [Initial deltoid injection of 234 mg followed by either 39 mg, 156 mg, or 234 mg every 4 weeks by deltoid or gluteal injection. Other dose groups (39 mg, 78 mg, and 156 mg) are from studies involving only gluteal injection. [see Clinical Studies (14.1)] .] | 234/156 mg | 234/234 mg
 | n=451 | n=116 | n=280 | n=267 | n=137 | n=144 | n=145
Weight (kg) Change from baseline | -0.4 | 0.4 | 0.8 | 1.4 | 0.4 | 0.7 | 1.4
Weight Gain ≥ 7% increase from baseline | 3.3% | 6.0% | 8.9% | 9.0% | 5.8% | 8.3% | 13.1%

In a long-term open-label pharmacokinetic and safety study in which the highest dose available (234 mg) was evaluated, INVEGA SUSTENNA was associated with a mean change in weight of +2.4 kg at Week 29 (n=134) and +4.3 kg at Week 53 (n=113).

During the initial 25-week open-label period of a long-term study in subjects with schizoaffective disorder, INVEGA SUSTENNA was associated with a mean change in weight of +2.2 kg and 18.4% of subjects had an increase in body weight of ≥ 7% (n=653). At the endpoint of the subsequent 15-month double-blind period of the study, INVEGA SUSTENNA was associated with a mean change in weight of -0.2 kg and 13.0% of subjects had an increase in body weight of ≥ 7% (n=161); the placebo group had a mean change in weight of -0.8 kg and 6.0% of subjects had an increase in body weight of ≥ 7% (n=168).

5.7 Orthostatic Hypotension and Syncope

Paliperidone can induce orthostatic hypotension and syncope in some patients because of its alpha-adrenergic blocking activity. Syncope was reported in < 1% (4/1293) of subjects treated with INVEGA SUSTENNA in the recommended dose range of 39 mg to 234 mg in the four fixed-dose, double-blind, placebo-controlled trials compared with 0% (0/510) of subjects treated with placebo. In the four fixed-dose efficacy studies in subjects with schizophrenia, orthostatic hypotension was reported as an adverse event by < 1% (2/1293) of INVEGA SUSTENNA-treated subjects compared to 0% (0/510) with placebo. Incidences of orthostatic hypotension and syncope in the long-term studies in subjects with schizophrenia and schizoaffective disorder were similar to those observed in the short-term studies.

INVEGA SUSTENNA should be used with caution in patients with known cardiovascular disease (e.g., heart failure, history of myocardial infarction or ischemia, conduction abnormalities), cerebrovascular disease, or conditions that predispose the patient to hypotension (e.g., dehydration, hypovolemia, and treatment with antihypertensive medications). Monitoring of orthostatic vital signs should be considered in patients who are vulnerable to hypotension.

5.8 Falls

Somnolence, postural hypotension, motor and sensory instability have been reported with the use of antipsychotics, including INVEGA SUSTENNA, which may lead to falls and, consequently, fractures or other fall-related injuries. For patients, particularly the elderly, with diseases, conditions, or medications that could exacerbate these effects, assess the risk of falls when initiating antipsychotic treatment and recurrently for patients on long-term antipsychotic therapy.

5.9 Leukopenia, Neutropenia, and Agranulocytosis

In clinical trial and/or postmarketing experience, events of leukopenia and neutropenia have been reported temporally related to antipsychotic agents, including INVEGA SUSTENNA. Agranulocytosis has also been reported.

Possible risk factors for leukopenia/neutropenia include pre-existing low white blood cell count (WBC)/absolute neutrophil count (ANC) and history of drug-induced leukopenia/neutropenia. In patients with a history of a clinically significant low WBC/ANC or a drug-induced leukopenia/neutropenia, perform a complete blood count (CBC) frequently during the first few months of therapy. In such patients, consider discontinuation of INVEGA SUSTENNA at the first sign of a clinically significant decline in WBC in the absence of other causative factors.

Monitor patients with clinically significant neutropenia for fever or other symptoms or signs of infection and treat promptly if such symptoms or signs occur. Discontinue INVEGA SUSTENNA in patients with severe neutropenia (absolute neutrophil count < 1000/mm^3) and follow their WBC until recovery.

5.10 Hyperprolactinemia

Like other drugs that antagonize dopamine D2 receptors, paliperidone elevates prolactin levels and the elevation persists during chronic administration. Paliperidone has a prolactin-elevating effect similar to that seen with risperidone, a drug that is associated with higher levels of prolactin than other antipsychotic drugs.

Hyperprolactinemia, regardless of etiology, may suppress hypothalamic GnRH, resulting in reduced pituitary gonadotrophin secretion. This, in turn, may inhibit reproductive function by impairing gonadal steroidogenesis in both female and male patients. Galactorrhea, amenorrhea, gynecomastia, and impotence have been reported in patients receiving prolactin-elevating compounds. Long-standing hyperprolactinemia when associated with hypogonadism may lead to decreased bone density in both female and male subjects.

Tissue culture experiments indicate that approximately one-third of human breast cancers are prolactin dependent in vitro, a factor of potential importance if the prescription of these drugs is considered in a patient with previously detected breast cancer. An increase in the incidence of pituitary gland, mammary gland, and pancreatic islet cell neoplasia (mammary adenocarcinomas, pituitary and pancreatic adenomas) was observed in the risperidone carcinogenicity studies conducted in mice and rats [see Nonclinical Toxicology (13.1)] . Published epidemiologic studies have shown inconsistent results when exploring the potential association between hyperprolactinemia and breast cancer.

Prolactin data from two long-term, double-blind, placebo-controlled studies with INVEGA SUSTENNA are presented below; one study was in a population of patients with schizophrenia; the second study was in patients with schizoaffective disorder.

Schizophrenia

In a long-term maintenance trial of INVEGA SUSTENNA in schizophrenia patients (Study PSY-3001), see Clinical Studies (14.1), elevations of prolactin to above the reference range (> 18 ng/mL in males and > 30 ng/mL in females) relative to open-label baseline at any time during the double-blind phase were noted in a higher percentage of the patients in the INVEGA SUSTENNA group than those in the placebo group in males (51.9% vs. 29.0%) and in females (50.5% vs. 42.9%). During the double-blind phase, 4 females (4.2%) in the INVEGA SUSTENNA group experienced potentially prolactin-related adverse reactions (amenorrhea N=2; galactorrhea N=1; menstruation irregular N=1), while 2 females (2.2%) in the placebo group experienced potentially prolactin-related adverse reactions (amenorrhea N=1; breast pain N=1). One male (0.9%) in the INVEGA SUSTENNA group experienced erectile dysfunction and 1 male (0.9%) in placebo group experienced gynecomastia.

Prior to the double-blind phase (during the 33-week open-label phase of the long-term maintenance trial), the mean (SD) serum prolactin values at baseline were 14.9 (22.3) ng/mL in males (N=490) and 35.2 (39.6) ng/mL in females (N=358). At the end of the open-label phase, mean (SD) prolactin values were 24.7 (22.5) ng/mL in males (N=470) and 59.5 (38.1) ng/mL in females (N=333). During the open-label phases 49.2% of females and 47.7% of males experienced elevations of prolactin above the reference range relative to baseline, and a higher proportion of females experienced potentially prolactin-related adverse reactions compared to males (5.3% vs. 1.8%). Amenorrhea (2.5%) in females and no single potentially prolactin-related adverse reaction in males were observed with a rate greater than 2%.

Schizoaffective Disorder

In a long-term maintenance trial of INVEGA SUSTENNA in patients with schizoaffective disorder (Study SCA-3004) see Clinical Studies (14.2), elevations of prolactin to above the reference range (> 13.13 ng/mL in males and > 26.72 ng/mL in females) relative to open-label baseline at any time during the 15-month double-blind phase were noted in a higher percentage of patients in the INVEGA SUSTENNA group than those in the placebo group in males (55.6% vs. 23.2%) and in females (44.3% vs. 25.0%). During the 15-month double-blind phase, 11 females (13.9%) in the INVEGA SUSTENNA group had 14 potentially prolactin-related adverse reactions (hyperprolactinemia N=3; blood prolactin increased N=4; libido decreased N=1; amenorrhea N=3; galactorrhea N=3), while 5 females (5.8%) in the placebo group had 6 potentially prolactin-related adverse reactions (hyperprolactinemia N=2; blood prolactin increased N=1; amenorrhea N=2; galactorrhea N=1). Six males (7.1%) in the INVEGA SUSTENNA group experienced 6 potentially prolactin-related adverse reactions (hyperprolactinemia N=4; libido decreased N=1; erectile dysfunction N=1), while 1 male (1.2%) in the placebo group experienced adverse reaction of blood prolactin increased.

Prior to the 15-month double-blind phase (during the 25-week open-label phase of the long-term maintenance trial), the mean (SD) serum prolactin values at baseline were 14.6 (14.0) ng/mL in males (N=352) and 39.1 (44.6) ng/mL in females (N=302). At the end of the open-label phase, mean (SD) prolactin values were 32.8 (17.2) ng/mL in males (N=275) and 72.4 (46.5) ng/mL in females (N=239). During the open-label phase, 48.9% of females and 53.3% of males experienced elevations of prolactin above the reference range relative to baseline, and a higher proportion of females experienced potentially prolactin-related adverse reactions compared to males (10.0% vs. 9.0%). Amenorrhea (5.8%) and galactorrhea (2.9%) in females and libido decrease (2.8%) and erectile dysfunction (2.5%) in males were observed with a rate greater than 2%.

5.11 Potential for Cognitive and Motor Impairment

Somnolence, sedation, and dizziness were reported as adverse reactions in subjects treated with INVEGA SUSTENNA [see Adverse Reactions (6.1)] . Antipsychotics, including INVEGA SUSTENNA, have the potential to impair judgment, thinking, or motor skills. Patients should be cautioned about performing activities requiring mental alertness, such as operating hazardous machinery or operating a motor vehicle, until they are reasonably certain that paliperidone therapy does not adversely affect them.

5.12 Seizures

In the four fixed-dose double-blind placebo-controlled studies in subjects with schizophrenia, <1% (1/1293) of subjects treated with INVEGA SUSTENNA in the recommended dose range of 39 mg to 234 mg experienced an adverse event of convulsion compared with <1% (1/510) of placebo-treated subjects who experienced an adverse event of grand mal convulsion.

Like other antipsychotic drugs, INVEGA SUSTENNA should be used cautiously in patients with a history of seizures or other conditions that potentially lower the seizure threshold. Conditions that lower the seizure threshold may be more prevalent in patients 65 years or older.

5.13 Dysphagia

Esophageal dysmotility and aspiration have been associated with antipsychotic drug use. INVEGA SUSTENNA and other antipsychotic drugs should be used cautiously in patients at risk for aspiration pneumonia.

5.14 Priapism

Drugs with alpha-adrenergic blocking effects have been reported to induce priapism. Although no cases of priapism have been reported in clinical trials with INVEGA SUSTENNA, priapism has been reported with oral paliperidone during postmarketing surveillance. Severe priapism may require surgical intervention.

5.15 Disruption of Body Temperature Regulation

Disruption of the body's ability to reduce core body temperature has been attributed to antipsychotic agents. Appropriate care is advised when prescribing INVEGA SUSTENNA to patients who will be experiencing conditions which may contribute to an elevation in core body temperature, e.g., exercising strenuously, exposure to extreme heat, receiving concomitant medication with anticholinergic activity, or being subject to dehydration.

6 ADVERSE REACTIONS

The following are discussed in more detail in other sections of the labeling:

- Increased mortality in elderly patients with dementia-related psychosis [see Boxed Warning and Warnings and Precautions (5.1)]
- Cerebrovascular adverse reactions, including stroke, in elderly patients with dementia-related psychosis [see Warnings and Precautions (5.2)]
- Neuroleptic malignant syndrome [see Warnings and Precautions (5.3)]
- QT prolongation [see Warnings and Precautions (5.4)]
- Tardive dyskinesia [see Warnings and Precautions (5.5)]
- Metabolic changes [see Warnings and Precautions (5.6)]
- Orthostatic hypotension and syncope [see Warnings and Precautions (5.7)]
- Falls [see Warnings and Precautions (5.8)]
- Leukopenia, neutropenia, and agranulocytosis [see Warnings and Precautions (5.9)]
- Hyperprolactinemia [see Warnings and Precautions (5.10)]
- Potential for cognitive and motor impairment [see Warnings and Precautions (5.11)]
- Seizures [see Warnings and Precautions (5.12)]
- Dysphagia [see Warnings and Precautions (5.13)]
- Priapism [see Warnings and Precautions (5.14)]
- Disruption of body temperature regulation [see Warnings and Precautions (5.15)]

6.1 Clinical Trials Experience

Because clinical trials are conducted under widely varying conditions, adverse reaction rates observed in the clinical trials of a drug cannot be directly compared to rates in the clinical trials of another drug and may not reflect the rates observed in clinical practice.

Patient Exposure

The data described in this section are derived from a clinical trial database consisting of a total of 3817 subjects (approximately 1705 patient-years exposure) with schizophrenia who received at least one dose of INVEGA SUSTENNA in the recommended dose range of 39 mg to 234 mg and a total of 510 subjects with schizophrenia who received placebo. Among the 3817 INVEGA SUSTENNA-treated subjects, 1293 received INVEGA SUSTENNA in four fixed-dose, double-blind, placebo-controlled trials (one 9-week and three 13-week studies), 849 received INVEGA SUSTENNA in the maintenance trial (median exposure 229 days during the initial 33-week open-label phase of this study, of whom 205 continued to receive INVEGA SUSTENNA during the double-blind placebo-controlled phase of this study [median exposure 171 days]), and 1675 received INVEGA SUSTENNA in five non-placebo controlled trials (three noninferiority active-comparator trials, one long-term open-label pharmacokinetic and safety study, and an injection site [deltoid-gluteal] cross-over trial). One of the 13-week studies included a 234 mg INVEGA SUSTENNA initiation dose followed by treatment with either 39 mg, 156 mg, or 234 mg every 4 weeks.

The safety of INVEGA SUSTENNA was also evaluated in a 15-month, long-term study comparing INVEGA SUSTENNA to selected oral antipsychotic therapies in adult subjects with schizophrenia. A total of 226 subjects received INVEGA SUSTENNA during the 15-month, open-label period of this study; 218 subjects received selected oral antipsychotic therapies. The safety of INVEGA SUSTENNA was similar to that seen in previous double-blind, placebo-controlled clinical trials in adult subjects with schizophrenia.

The safety of INVEGA SUSTENNA was also evaluated in a long-term study in adult subjects with schizoaffective disorder. A total of 667 subjects received INVEGA SUSTENNA during the initial 25-week open-label period of this study (median exposure 147 days); 164 subjects continued to receive INVEGA SUSTENNA during the 15-month double-blind placebo-controlled period of this study (median exposure 446 days). Adverse reactions that occurred more frequently in the INVEGA SUSTENNA than the placebo group (a 2% difference or more between groups) were weight increased, nasopharyngitis, headache, hyperprolactinemia, and pyrexia.

Adverse Reactions in Double-Blind, Placebo-Controlled Clinical Trials

Commonly Observed Adverse Reactions: The most common (at least 5% in any INVEGA SUSTENNA group) and likely drug-related (adverse events for which the drug rate is at least twice the placebo rate) adverse reactions from the double-blind, placebo-controlled trials in subjects with schizophrenia were injection site reactions, somnolence/sedation, dizziness, akathisia, and extrapyramidal disorder .No occurrences of adverse events reached this threshold in the long-term double-blind, placebo-controlled study in subjects with schizoaffective disorder.

Discontinuation of Treatment Due to Adverse Events: The percentage of subjects who discontinued due to adverse events in the four fixed-dose, double-blind, placebo-controlled schizophrenia trials were similar for INVEGA SUSTENNA- and placebo-treated subjects.

The percentage of subjects who discontinued due to adverse events in the open-label period of the long-term study in subjects with schizoaffective disorder was 7.5%. During the double-blind, placebo-controlled period of that study, the percentages of subjects who discontinued due to adverse events were 5.5% and 1.8% in INVEGA SUSTENNA- and placebo-treated subjects, respectively.

Dose-Related Adverse Reactions: Based on the pooled data from the four fixed-dose, double-blind, placebo-controlled trials in subjects with schizophrenia, among the adverse reactions that occurred with ≥ 2% incidence in the subjects treated with INVEGA SUSTENNA, only akathisia increased with dose. Hyperprolactinemia also exhibited a dose relationship, but did not occur at ≥ 2% incidence in INVEGA SUSTENNA-treated subjects from the four fixed-dose studies.

Adverse Reactions Occurring at an Incidence of 2% or More in INVEGA SUSTENNA-Treated Patients: Table 10 lists the adverse reactions reported in 2% or more of INVEGA SUSTENNA-treated subjects and at a greater proportion than in the placebo group with schizophrenia in the four fixed-dose, double-blind, placebo-controlled trials.

Table 10: Incidences of Adverse Reactions 2% or More of INVEGA SUSTENNA-Treated Patients (and Greater than Placebo) with Schizophrenia in Four Fixed-Dose, Double-Blind, Placebo-Controlled Trials
 |  | INVEGA SUSTENNA
System Organ Class | Placebo [Placebo group is pooled from all studies and included either deltoid or gluteal injection depending on study design.] | 39 mg | 78 mg | 156 mg | 234/39 mg [Initial deltoid injection of 234 mg followed by either 39 mg, 156 mg, or 234 mg every 4 weeks by deltoid or gluteal injection. Other dose groups (39 mg, 78 mg, and 156 mg) are from studies involving only gluteal injection. [see Clinical Studies (14.1)]] | 234/156 mg | 234/234 mg
Adverse Reactions | (N=510) | (N=130) | (N=302) | (N=312) | (N=160) | (N=165) | (N=163)
Total percentage of subjects with adverse reactions | 70 | 75 | 68 | 69 | 63 | 60 | 63
Gastrointestinal disorders
Abdominal discomfort/abdominal pain upper | 2 | 2 | 4 | 4 | 1 | 2 | 4
Diarrhea | 2 | 0 | 3 | 2 | 1 | 2 | 2
Dry mouth | 1 | 3 | 1 | 0 | 1 | 1 | 1
Nausea | 3 | 4 | 4 | 3 | 2 | 2 | 2
Toothache | 1 | 1 | 1 | 3 | 1 | 2 | 3
Vomiting | 4 | 5 | 4 | 2 | 3 | 2 | 2
General disorders and administration site conditions
Asthenia | 0 | 2 | 1 | <1 | 0 | 1 | 1
Fatigue | 1 | 1 | 2 | 2 | 1 | 2 | 1
Injection site reactions | 2 | 0 | 4 | 6 | 9 | 7 | 10
Infections and infestations
Nasopharyngitis | 2 | 0 | 2 | 2 | 4 | 2 | 2
Upper respiratory tract infection | 2 | 2 | 2 | 2 | 1 | 2 | 4
Urinary tract infection | 1 | 0 | 1 | <1 | 1 | 1 | 2
Investigations
Weight increased | 1 | 4 | 4 | 1 | 1 | 1 | 2
Musculoskeletal and connective tissue disorders
Back pain | 2 | 2 | 1 | 3 | 1 | 1 | 1
Musculoskeletal stiffness | 1 | 1 | <1 | <1 | 1 | 1 | 2
Myalgia | 1 | 2 | 1 | <1 | 1 | 0 | 2
Pain in extremity | 1 | 0 | 2 | 2 | 2 | 3 | 0
Nervous system disorders
Akathisia | 3 | 2 | 2 | 3 | 1 | 5 | 6
Dizziness | 1 | 6 | 2 | 4 | 1 | 4 | 2
Extrapyramidal disorder | 1 | 5 | 2 | 3 | 1 | 0 | 0
Headache | 12 | 11 | 11 | 15 | 11 | 7 | 6
Somnolence/sedation | 3 | 5 | 7 | 4 | 1 | 5 | 5
Psychiatric disorders
Agitation | 7 | 10 | 5 | 9 | 8 | 5 | 4
Anxiety | 7 | 8 | 5 | 3 | 5 | 6 | 6
Nightmare | <1 | 2 | 0 | 0 | 0 | 0 | 0
Respiratory, thoracic and mediastinal disorders
Cough | 1 | 2 | 3 | 1 | 0 | 1 | 1
Vascular disorders
Hypertension | 1 | 2 | 1 | 1 | 1 | 1 | 0
Percentages are rounded to whole numbers. Table includes adverse reactions that were reported in 2% or more of subjects in any of the INVEGA SUSTENNA dose groups and which occurred at greater incidence than in the placebo group.

Adverse reactions for which the INVEGA SUSTENNA incidence was equal to or less than placebo are not listed in the table, but included the following: dyspepsia, psychotic disorder, schizophrenia, and tremor. The following terms were combined: somnolence/sedation, breast tenderness/breast pain, abdominal discomfort/abdominal pain upper/stomach discomfort, and tachycardia/sinus tachycardia/heart rate increased. All injection site reaction-related adverse reactions were collapsed and are grouped under "Injection site reactions".

Other Adverse Reactions Observed During the Clinical Trial Evaluation of INVEGA SUSTENNA

The following list does not include reactions: 1) already listed in previous tables or elsewhere in labeling, 2) for which a drug cause was remote, 3) which were so general as to be uninformative, or 4) which were not considered to have significant clinical implications.

Cardiac disorders: atrioventricular block first degree, bradycardia, bundle branch block, palpitations, postural orthostatic tachycardia syndrome, tachycardia

Ear and labyrinth disorders: vertigo

Eye disorders: eye movement disorder, eye rolling, oculogyric crisis, vision blurred

Gastrointestinal disorders: constipation, dyspepsia, flatulence, salivary hypersecretion

Immune system disorders: hypersensitivity

Investigations: alanine aminotransferase increased, aspartate aminotransferase increased, electrocardiogram abnormal

Metabolism and nutrition disorders: decreased appetite, hyperinsulinemia, increased appetite

Musculoskeletal and connective tissue disorders: arthralgia, joint stiffness, muscle rigidity, muscle spasms, muscle tightness, muscle twitching, nuchal rigidity

Nervous system disorders: bradykinesia, cerebrovascular accident, cogwheel rigidity, convulsion, dizziness postural, drooling, dysarthria, dyskinesia, dystonia, hypertonia, lethargy, oromandibular dystonia, parkinsonism, psychomotor hyperactivity, syncope

Psychiatric disorders: insomnia, libido decreased, restlessness

Reproductive system and breast disorders: amenorrhea, breast discharge, breast enlargement/breast swelling, breast tenderness/breast pain, ejaculation disorder, erectile dysfunction, galactorrhea, gynecomastia, menstrual disorder, menstruation delayed, menstruation irregular, sexual dysfunction

Respiratory, thoracic and mediastinal disorders: nasal congestion

Skin and subcutaneous tissue disorders: drug eruption, pruritus, pruritus generalized, rash, urticaria

Demographic Differences

An examination of population subgroups in the double-blind placebo-controlled trials did not reveal any evidence of differences in safety on the basis of age, gender, or race alone; however, there were few subjects 65 years of age and older.

Extrapyramidal Symptoms (EPS)

Pooled data from the two double-blind, placebo-controlled, 13-week, fixed-dose trials in adult subjects with schizophrenia provided information regarding EPS. Several methods were used to measure EPS: (1) the Simpson-Angus global score which broadly evaluates parkinsonism, (2) the Barnes Akathisia Rating Scale global clinical rating score which evaluates akathisia, (3) the Abnormal Involuntary Movement Scale scores which evaluates dyskinesia, and (4) use of anticholinergic medications to treat EPS (Table 11), and (5) incidence of spontaneous reports of EPS (Table 12).

Table 11: Extrapyramidal Symptoms (EPS) Assessed by Incidence of Rating Scales and Use of Anticholinergic Medication – Schizophrenia Studies in Adults
 | Percentage of Subjects
 |  | INVEGA SUSTENNA
Scale | Placebo (N=262) | 39 mg (N=130) | 78 mg (N=223) | 156 mg (N=228)
Parkinsonism [For parkinsonism, percent of subjects with Simpson-Angus Total score > 0.3 at endpoint (Total score defined as total sum of items score divided by the number of items)] | 9 | 12 | 10 | 6
Akathisia [For Akathisia, percent of subjects with Barnes Akathisia Rating Scale global score ≥ 2 at endpoint] | 5 | 5 | 6 | 5
Dyskinesia [For Dyskinesia, percent of subjects with a score ≥ 3 on any of the first 7 items or a score ≥ 2 on two or more of any of the first 7 items of the Abnormal Involuntary Movement Scale at endpoint] | 3 | 4 | 6 | 4
Use of Anticholinergic Medications [Percent of subjects who received anticholinergic medications to treat EPS] | 12 | 10 | 12 | 11

Table 12: Extrapyramidal Symptoms (EPS)-Related Events by MedDRA Preferred Term – Schizophrenia Studies in Adults
 | Percentage of Subjects
 |  | INVEGA SUSTENNA
EPS Group | Placebo (N=262) | 39 mg (N=130) | 78 mg (N=223) | 156 mg (N=228)
Overall percentage of subjects with EPS-related adverse events | 10 | 12 | 11 | 11
Parkinsonism | 5 | 6 | 6 | 4
Hyperkinesia | 2 | 2 | 2 | 4
Tremor | 3 | 2 | 2 | 3
Dyskinesia | 1 | 2 | 3 | 1
Dystonia | 0 | 1 | 1 | 2
Parkinsonism group includes: Extrapyramidal disorder, hypertonia, musculoskeletal stiffness, parkinsonism, drooling, masked facies, muscle tightness, hypokinesia
Hyperkinesia group includes: Akathisia, restless legs syndrome, restlessness
Dyskinesia group includes: Dyskinesia, choreoathetosis, muscle twitching, myoclonus, tardive dyskinesia
Dystonia group includes: Dystonia, muscle spasms

The results across all phases of the maintenance trial in subjects with schizophrenia exhibited comparable findings. In the 9-week, fixed-dose, double-blind, placebo-controlled trial, the proportions of parkinsonism and akathisia assessed by incidence of rating scales were higher in the INVEGA SUSTENNA 156 mg group (18% and 11%, respectively) than in the INVEGA SUSTENNA 78 mg group (9% and 5%, respectively) and placebo group (7% and 4%, respectively).

In the 13-week study in subjects with schizophrenia involving 234 mg initiation dosing, the incidence of any EPS was similar to that of the placebo group (8%), but exhibited a dose-related pattern with 6%, 10%, and 11% in the INVEGA SUSTENNA 234/39 mg, 234/156 mg, and 234/234 mg groups, respectively. Hyperkinesia was the most frequent category of EPS-related adverse events in this study, and was reported at a similar rate between the placebo (4.9%) and INVEGA SUSTENNA 234/156 mg (4.8%) and 234/234 mg (5.5%) groups, but at a lower rate in the 234/39 mg group (1.3%).

In the long-term study in subjects with schizoaffective disorder, EPS reported during the 25-week open-label INVEGA SUSTENNA treatment included hyperkinesia (12.3%), parkinsonism (8.7%), tremor (3.4%), dyskinesia (2.5%), and dystonia (2.1%). During the 15-month double-blind treatment, the incidence of any EPS was similar to that of the placebo group (8.5% and 7.1% respectively). The most commonly reported treatment-emergent EPS-related adverse events (> 2%) in any treatment group in the double-blind phase of the study (INVEGA SUSTENNA versus placebo) were hyperkinesia (3.7% vs. 2.9%), parkinsonism (3.0% vs. 1.8%), and tremor (1.2% vs. 2.4%).

Dystonia

Symptoms of dystonia, prolonged abnormal contractions of muscle groups, may occur in susceptible individuals during the first few days of treatment. Dystonic symptoms include: spasm of the neck muscles, sometimes progressing to tightness of the throat, swallowing difficulty, difficulty breathing, and/or protrusion of the tongue. While these symptoms can occur at low doses, they occur more frequently and with greater severity with high potency and at higher doses of first generation antipsychotic drugs. An elevated risk of acute dystonia is observed in males and younger age groups.

Pain Assessment and Local Injection Site Reactions

In the pooled data from the two 13-week, fixed-dose, double-blind, placebo-controlled trials in subjects with schizophrenia, the mean intensity of injection pain reported by subjects using a visual analog scale (0 = no pain to 100 = unbearably painful) decreased in all treatment groups from the first to the last injection (placebo: 10.9 to 9.8; 39 mg: 10.3 to 7.7; 78 mg: 10.0 to 9.2; 156 mg: 11.1 to 8.8). The results from both the 9-week, fixed-dose, double-blind, placebo-controlled trial and the double-blind phase of the maintenance trial exhibited comparable findings.

In the 13-week study involving 234 mg initiation dosing in subjects with schizophrenia, occurrences of induration, redness, or swelling, as assessed by blinded study personnel, were infrequent, generally mild, decreased over time, and similar in incidence between the INVEGA SUSTENNA and placebo groups. Investigator ratings of injection pain were similar for the placebo and INVEGA SUSTENNA groups. Investigator evaluations of the injection site after the first injection for redness, swelling, induration, and pain were rated as absent for 69–100% of subjects in both the INVEGA SUSTENNA and placebo groups. At Day 92, investigators rated absence of redness, swelling, induration, and pain in 95–100% of subjects in both the INVEGA SUSTENNA and placebo groups.

Additional Adverse Reactions Reported in Clinical Trials with Oral Paliperidone

The following is a list of additional adverse reactions that have been reported in clinical trials with oral paliperidone:

Cardiac disorders: bundle branch block left, sinus arrhythmia

Gastrointestinal disorders: abdominal pain, small intestinal obstruction

General disorders and administration site conditions: edema, edema peripheral

Immune system disorders: anaphylactic reaction

Infections and infestations: rhinitis

Musculoskeletal and connective tissue disorders: musculoskeletal pain, torticollis, trismus

Nervous system disorders: grand mal convulsion, parkinsonian gait, transient ischemic attack

Psychiatric disorders: sleep disorder

Reproductive system and breast disorders: breast engorgement

Respiratory, thoracic and mediastinal disorders: pharyngolaryngeal pain, pneumonia aspiration

Skin and subcutaneous tissue disorders: rash papular

Vascular disorders: hypotension, ischemia

6.2 Postmarketing Experience

The following adverse reactions have been identified during postapproval use of paliperidone; because these reactions were reported voluntarily from a population of uncertain size, it is not always possible to reliably estimate their frequency or establish a causal relationship to drug exposure: angioedema, catatonia, ileus, somnambulism, swollen tongue, thrombotic thrombocytopenic purpura, urinary incontinence, and urinary retention.

Cases of anaphylactic reaction after injection with INVEGA SUSTENNA have been reported during postmarketing experience in patients who have previously tolerated oral risperidone or oral paliperidone.

Paliperidone is the major active metabolite of risperidone. Adverse reactions reported with oral risperidone and risperidone long-acting injection can be found in the Adverse Reactions (6)sections of the package inserts for those products.

7 DRUG INTERACTIONS

7.1 Drugs Having Clinically Important Interactions with INVEGA SUSTENNA

Because paliperidone palmitate is hydrolyzed to paliperidone [see Clinical Pharmacology (12.3)] , results from studies with oral paliperidone should be taken into consideration when assessing drug-drug interaction potential.

Table 13. Clinically Important Drug Interactions with INVEGA SUSTENNA
Concomitant Drug Name or Drug Class | Clinical Rationale | Clinical Recommendation
Centrally Acting Drugs and Alcohol | Given the primary CNS effects of paliperidone, concomitant use of centrally acting drugs and alcohol may modulate the CNS effects of INVEGA SUSTENNA. | INVEGA SUSTENNA should be used with caution in combination with other centrally acting drugs and alcohol [see Adverse Reactions (6.1, 6.2)] .
Drugs with Potential for Inducing Orthostatic Hypotension | Because INVEGA SUSTENNA has the potential for inducing orthostatic hypotension, an additive effect may occur when INVEGA SUSTENNA is administered with other therapeutic agents that have this potential [see Warnings and Precautions (5.7)] . | Monitor orthostatic vital signs in patients who are vulnerable to hypotension [see Warnings and Precautions (5.7)] .
Strong Inducers of CYP3A4 and P-gp (e.g., carbamazepine, rifampin, or St. John's Wort) | The concomitant use of paliperidone and strong inducers of CYP3A4 and P-gp may decrease the exposure of paliperidone [see Clinical Pharmacology (12.3)] . | Avoid using CYP3A4 and/or P-gp inducers with INVEGA SUSTENNA during the 1-month dosing interval, if possible. If administering a strong inducer is necessary, consider managing the patient using paliperidone extended-release tablets [see Dosage and Administration (2.5)] .
Levodopa and Other Dopamine Agonists | Paliperidone may antagonize the effect of levodopa and other dopamine agonists. | Monitor and manage patient as clinically appropriate.

7.2 Drugs Having No Clinically Important Interactions with INVEGA SUSTENNA

Clinically meaningful pharmacokinetic interaction between INVEGA SUSTENNA and valproate (including valproic acid and divalproex sodium) is not expected. Based on pharmacokinetic studies with oral paliperidone, no dosage adjustment of INVEGA SUSTENNA is required when administered with valproate [see Clinical Pharmacology (12.3)]. Additionally, no dosage adjustment is necessary for valproate when co-administered with INVEGA SUSTENNA [See Clinical Pharmacology (12.3)].

Pharmacokinetic interaction between lithium and INVEGA SUSTENNA is also unlikely.

Paliperidone is not expected to cause clinically important pharmacokinetic interactions with drugs that are metabolized by cytochrome P450 isozymes. In vitro studies indicate that CYP2D6 and CYP3A4 may be involved in paliperidone metabolism; however, there is no evidence in vivo that inhibitors of these enzymes significantly affect the metabolism of paliperidone. Paliperidone is not a substrate of CYP1A2, CYP2A6, CYP2C9, and CYP2C19; an interaction with inhibitors or inducers of these isozymes is unlikely. [see Clinical Pharmacology (12.3)]

8 USE IN SPECIFIC POPULATIONS

8.1 Pregnancy

Pregnancy Exposure Registry

There is a pregnancy exposure registry that monitors pregnancy outcomes in women exposed to atypical antipsychotics, including INVEGA SUSTENNA, during pregnancy. Healthcare providers are encouraged to register patients by contacting the National Pregnancy Registry for Atypical Antipsychotics at 1-866-961-2388 or online at http://womensmentalhealth.org/clinical-and-research-programs/pregnancyregistry/.

Risk Summary

Neonates exposed to antipsychotic drugs during the third trimester of pregnancy are at risk for extrapyramidal and/or withdrawal symptoms following delivery (see Clinical Considerations) . Overall, available data from published epidemiologic studies of pregnant women exposed to paliperidone have not established a drug-associated risk for major birth defects, miscarriage, or adverse maternal or fetal outcomes (see Data) . There are risks to the mother associated with untreated schizophrenia and with exposure to antipsychotics, including INVEGA SUSTENNA, during pregnancy (see Clinical Considerations). Paliperidone has been detected in plasma in adult subjects up to 126 days after a single-dose administration of INVEGA SUSTENNA [see Clinical Pharmacology (12.3)] , and the clinical significance of INVEGA SUSTENNA administered before pregnancy or anytime during pregnancy is not known.

The estimated background risk of major birth defects and miscarriage for the indicated population is unknown. All pregnancies have a background risk of birth defects, loss, or other adverse outcomes. In the U.S. general population, the estimated background risk of major birth defects and miscarriage in clinically recognized pregnancies is 2–4% and 15–20%, respectively.

In animal reproduction studies, there were no treatment related effects on the offspring when pregnant rats were injected intramuscularly with paliperidone palmitate during the period of organogenesis at doses up to 10 times the maximum recommended human dose (MRHD) of 234 mg paliperidone based on mg/m^2 body surface area. There were no increases in fetal abnormalities when pregnant rats and rabbits were treated orally with paliperidone during the period of organogenesis with up to 8 times the MRHD of 12 mg of paliperidone based on mg/m^2 body surface area. Additional reproduction toxicity studies were conducted with orally administered risperidone, which is extensively converted to paliperidone (see Animal data).

Clinical Considerations

Disease-associated maternal and/or embryo/fetal risk

There is a risk to the mother from untreated schizophrenia, including increased risk of relapse, hospitalization, and suicide. Schizophrenia and bipolar I disorder are associated with increased adverse perinatal outcomes, including preterm birth. It is not known if this is a direct result of the illness or other comorbid factors.

Fetal/Neonatal Adverse Reactions

Extrapyramidal and/or withdrawal symptoms, including agitation, hypertonia, hypotonia, tremor, somnolence, respiratory distress, and feeding disorder have been reported in neonates who were exposed to antipsychotic drugs, including INVEGA SUSTENNA, during the third trimester of pregnancy. These symptoms have varied in severity. Monitor neonates exhibiting extrapyramidal and/or withdrawal symptoms and manage symptoms appropriately. Some neonates recovered within hours or days without specific treatment; others required prolonged hospitalization.

Data

Human Data

Published data from observational studies, birth registries, and case reports on the use of atypical antipsychotics during pregnancy do not report a clear association with antipsychotics and major birth defects. A prospective observational study including 6 women treated with risperidone, the parent compound of paliperidone, demonstrated placental passage of risperidone and paliperidone. A retrospective cohort study from a Medicaid database of 9258 women exposed to antipsychotics during pregnancy did not indicate an overall increased risk for major birth defects. There was a small increase in the risk of major birth defects (RR= 1.26, 95% CI 1.02–1.56) and of cardiac malformations (RR=1.26, 95% CI 0.88–1.81) in a subgroup of 1566 women exposed to the parent compound of paliperidone, risperidone, during the first trimester of pregnancy; however, there is no mechanism of action to explain the difference in malformation rates.

Animal Data

There were no treatment-related effects on the offspring when pregnant rats were injected intramuscularly with paliperidone palmitate extended-release injectable suspension during the period of organogenesis at doses up to 250 mg/kg, which is 10 times MRHD of 234 mg paliperidone based on mg/m^2 body surface area.

In animal reproduction studies, there were no increases in fetal abnormalities when pregnant rats and rabbits were treated orally with paliperidone during the period of organogenesis with up to 8 times the MRHD of 12 mg based on mg/m^2 body surface area.

Additional reproduction toxicity studies were conducted with orally administered risperidone, which is extensively converted to paliperidone. Cleft palate was observed in the offspring of pregnant mice treated with risperidone at 3 to 4 times the MRHD of 16 mg based on mg/m^2 body surface area; maternal toxicity occurred at 4 times the MHRD. There was no evidence of teratogenicity in embryo-fetal developmental toxicity studies with risperidone in rats and rabbits at doses up to 6 times the MRHD of 16 mg/day risperidone based on mg/m^2 body surface area. When the offspring of pregnant rats, treated with risperidone at 0.6 times the MRHD based on mg/m^2body surface area, reached adulthood, learning was impaired. Increased neuronal cell death occurred in the fetal brains of the offspring of pregnant rats treated at 0.5 to 1.2 times the MRHD; the postnatal development and growth of the offspring was delayed.

In rat reproduction studies with risperidone, pup deaths occurred at oral doses which are less than the MRHD of risperidone based on mg/m^2 body surface area; it is not known whether these deaths were due to a direct effect on the fetuses or pups or, to effects on the dams (see RISPERDAL package insert).

8.2 Lactation

Risk Summary

Limited data from published literature report the presence of paliperidone in human breast milk. There is no information on the effects on the breastfed infant or the effects on milk production; however, there are reports of sedation, failure to thrive, jitteriness, and extrapyramidal symptoms (tremors and abnormal muscle movements) in breastfed infants exposed to paliperidone's parent compound, risperidone (see Clinical Considerations) . Paliperidone has been detected in plasma in adult subjects up to 126 days after a single-dose administration of INVEGA SUSTENNA [see Clinical Pharmacology (12.3)] , and the clinical significance on the breastfed infant is not known. The developmental and health benefits of breastfeeding should be considered along with the mother's clinical need for INVEGA SUSTENNA and any potential adverse effects on the breastfed child from INVEGA SUSTENNA or from the mother's underlying condition.

Clinical Considerations

Infants exposed to INVEGA SUSTENNA through breastmilk should be monitored for excess sedation, failure to thrive, jitteriness, and extrapyramidal symptoms (tremors and abnormal muscle movements).

8.3 Females and Males of Reproductive Potential

Infertility

Females

Based on the pharmacologic action of paliperidone (D2 receptor antagonism), treatment with INVEGA SUSTENNA may result in an increase in serum prolactin levels, which may lead to a reversible reduction in fertility in females of reproductive potential [see Warnings and Precautions (5.10)].

8.4 Pediatric Use

Safety and effectiveness of INVEGA SUSTENNA in patients < 18 years of age have not been established.

Juvenile Animal Studies

In a study in which juvenile rats were treated with oral paliperidone from days 24 to 73 of age, a reversible impairment of performance in a test of learning and memory was seen, in females only, with a no-effect dose of 0.63 mg/kg/day, which produced plasma levels (AUC) of paliperidone similar to those in adolescents dosed at 12 mg/day. No other consistent effects on neurobehavioral or reproductive development were seen up to the highest dose tested (2.5 mg/kg/day), which produced plasma levels of paliperidone 2–3 times those in adolescents.

Juvenile dogs were treated for 40 weeks with oral risperidone, which is extensively metabolized to paliperidone in animals and humans, at doses of 0.31, 1.25, or 5 mg/kg/day. Decreased bone length and density were seen with a no-effect dose of 0.31 mg/kg/day, which produced plasma levels (AUC) of risperidone plus paliperidone which were similar to those in children and adolescents receiving the MRHD of risperidone. In addition, a delay in sexual maturation was seen at all doses in both males and females. The above effects showed little or no reversibility in females after a 12-week drug-free recovery period.

The long-term effects of INVEGA SUSTENNA on growth and sexual maturation have not been fully evaluated in children and adolescents.

8.5 Geriatric Use

Clinical studies of INVEGA SUSTENNA did not include sufficient numbers of subjects aged 65 and over to determine whether they respond differently from younger subjects. Other reported clinical experience has not identified differences in responses between the elderly and younger patients.

This drug is known to be substantially excreted by the kidney and clearance is decreased in patients with renal impairment [see Clinical Pharmacology (12.3)] , who should be given reduced doses. Because elderly patients are more likely to have decreased renal function, adjust dose based on renal function [see Dosage and Administration (2.5)].

8.6 Renal Impairment

Use of INVEGA SUSTENNA is not recommended in patients with moderate or severe renal impairment (creatinine clearance < 50 mL/min). Dose reduction is recommended for patients with mild renal impairment (creatinine clearance ≥ 50 mL/min to < 80 mL/min) [see Dosage and Administration (2.5) and Clinical Pharmacology (12.3)] .

8.7 Hepatic Impairment

INVEGA SUSTENNA has not been studied in patients with hepatic impairment. Based on a study with oral paliperidone, no dose adjustment is required in patients with mild or moderate hepatic impairment. Paliperidone has not been studied in patients with severe hepatic impairment [see Clinical Pharmacology (12.3)] .

8.8 Patients with Parkinson's Disease or Lewy Body Dementia

Patients with Parkinson's Disease or Dementia with Lewy Bodies can experience increased sensitivity to INVEGA SUSTENNA. Manifestations can include confusion, obtundation, postural instability with frequent falls, extrapyramidal symptoms, and clinical features consistent with neuroleptic malignant syndrome.

9 DRUG ABUSE AND DEPENDENCE

9.1 Controlled Substance

INVEGA SUSTENNA (paliperidone) is not a controlled substance.

9.2 Abuse

Paliperidone has not been systematically studied in animals or humans for its potential for abuse.

9.3 Dependence

Paliperidone has not been systematically studied in animals or humans for its potential for tolerance or physical dependence.

10 OVERDOSAGE

10.1 Human Experience

No cases of overdose were reported in premarketing studies with INVEGA SUSTENNA. Because INVEGA SUSTENNA is to be administered by healthcare professionals, the potential for overdosage by patients is low.

While experience with paliperidone overdose is limited, among the few cases of overdose reported in premarketing trials with oral paliperidone, the highest estimated ingestion was 405 mg. Observed signs and symptoms included extrapyramidal symptoms and gait unsteadiness. Other potential signs and symptoms include those resulting from an exaggeration of paliperidone's known pharmacological effects, i.e., drowsiness and sedation, tachycardia and hypotension, and QT prolongation. Torsades de pointes and ventricular fibrillation have been reported in a patient in the setting of overdose with oral paliperidone.

Paliperidone is the major active metabolite of risperidone. Overdose experience reported with risperidone can be found in the OVERDOSAGE section of the risperidone package insert.

10.2 Management of Overdosage

Contact a Certified Poison Control Center for the most up to date information on the management of INVEGA SUSTENNA overdosage (1-800-222-1222 or www.poison.org). Provide supportive care, including close medical supervision and monitoring. Treatment should consist of general measures employed in the management of overdosage with any drug. Consider the possibility of multiple drug overdosage. Ensure an adequate airway, oxygenation, and ventilation. Monitor cardiac rhythm and vital signs. Use supportive and symptomatic measures. There is no specific antidote to paliperidone.

Consider the prolonged-release characteristics of INVEGA SUSTENNA and the long apparent half-life of paliperidone when assessing treatment needs and recovery.

11 DESCRIPTION

INVEGA SUSTENNA® contains paliperidone palmitate. The active ingredient, paliperidone, is an atypical antipsychotic belonging to the chemical class of benzisoxazole derivatives. INVEGA SUSTENNA contains a racemic mixture of (+)- and (-)- paliperidone palmitate. The chemical name is (9 RS)-3-[2-[4-(6-Fluoro-1,2-benzisoxazol-3-yl)piperidin-1-yl]ethyl]-2-methyl-4-oxo-6,7,8,9-tetrahydro-4 H-pyrido[1,2- a]pyrimadin-9-yl hexadecanoate. Its molecular formula is C39H57FN4O4 and its molecular weight is 664.89. The structural formula is:

Paliperidone palmitate is very slightly soluble in ethanol and methanol, practically insoluble in polyethylene glycol 400 and propylene glycol, and slightly soluble in ethyl acetate.

INVEGA SUSTENNA is available as a white to off-white sterile aqueous extended-release suspension for intramuscular injection in the following dose strengths of paliperidone palmitate (and deliverable volumes) of the single-dose prefilled syringes: 39 mg (0.25 mL), 78 mg (0.5 mL), 117 mg (0.75 mL), 156 mg (1.0 mL), and 234 mg (1.5 mL). The drug product hydrolyzes to the active moiety, paliperidone, resulting in dose strengths of 25 mg, 50 mg, 75 mg, 100 mg, and 150 mg of paliperidone, respectively. The inactive ingredients are polysorbate 20 (12 mg/mL), polyethylene glycol 4000 (30 mg/mL), citric acid monohydrate (5 mg/mL), disodium hydrogen phosphate anhydrous (5 mg/mL), sodium dihydrogen phosphate monohydrate (2.5 mg/mL), sodium hydroxide (2.84 mg/mL used as an alkalizing agent to set pH at 7), and water for injection.

INVEGA SUSTENNA is provided in a single-dose prefilled syringe (cyclic-olefin-copolymer) with a plunger stopper and tip cap (bromobutyl rubber). The kit also contains 2 safety needles (a 1 ½-inch 22 gauge safety needle and a 1-inch 23 gauge safety needle).

12 CLINICAL PHARMACOLOGY

12.1 Mechanism of Action

Paliperidone palmitate is hydrolyzed to paliperidone [see Clinical Pharmacology (12.3)] . Paliperidone is the major active metabolite of risperidone. The mechanism of action of paliperidone is unclear. However, the drug's therapeutic effect in schizophrenia could be mediated through a combination of central dopamine Type 2 (D2) and serotonin Type 2 (5HT2A) receptor antagonism.

12.2 Pharmacodynamics

In vitro, paliperidone acts as an antagonist at the central dopamine Type 2 (D2) and serotonin Type 2 (5HT2A) receptors with binding affinities (Ki values) of 1.6–2.8 nM for D2 and 0.8–1.2 nM for 5HT2A receptors. Paliperidone is also active as an antagonist at histamine H1 and α1 and α2 adrenergic receptors with binding affinities of 32 nM, 4 nM, 17 nM, respectively. Paliperidone has no affinity for cholinergic muscarinic or β1- and β2-adrenergic receptors. The pharmacological activity of the (+)- and (-)- paliperidone enantiomers is qualitatively and quantitatively similar .

12.3 Pharmacokinetics

Absorption and Distribution

Due to its extremely low water solubility, the 1-month formulation of paliperidone palmitate dissolves slowly after intramuscular injection before being hydrolyzed to paliperidone and absorbed into the systemic circulation. Following a single intramuscular dose, the plasma concentrations of paliperidone gradually rise to reach maximum plasma concentrations at a median Tmax of 13 days. The release of the drug starts as early as day 1 and lasts for as long as 126 days.

Following intramuscular injection of single doses (39 mg – 234 mg) in the deltoid muscle, on average, a 28% higher Cmax was observed compared with injection in the gluteal muscle. The two initial deltoid intramuscular injections of 234 mg on day 1 and 156 mg on day 8 help attain therapeutic concentrations rapidly. The release profile and dosing regimen of INVEGA SUSTENNA results in sustained therapeutic concentrations. The AUC of paliperidone following INVEGA SUSTENNA administration was dose-proportional over a 39 mg-234 mg dose range, and less than dose-proportional for Cmax for doses exceeding 78 mg. The mean steady-state peak: trough ratio for an INVEGA SUSTENNA dose of 156 mg was 1.8 following gluteal administration and 2.2 following deltoid administration.

Following administration of paliperidone palmitate the (+) and (-) enantiomers of paliperidone interconvert, reaching an AUC (+) to (-) ratio of approximately 1.6–1.8.

Based on a population analysis, the apparent volume of distribution of paliperidone is 391 L. The plasma protein binding of racemic paliperidone is 74%.

Metabolism and Elimination

In a study with oral immediate-release^14C-paliperidone, one week following administration of a single oral dose of 1 mg immediate-release^14C-paliperidone, 59% of the dose was excreted unchanged into urine, indicating that paliperidone is not extensively metabolized in the liver. Approximately 80% of the administered radioactivity was recovered in urine and 11% in the feces. Four metabolic pathways have been identified in vivo, none of which accounted for more than 10% of the dose: dealkylation, hydroxylation, dehydrogenation, and benzisoxazole scission. Although in vitro studies suggested a role for CYP2D6 and CYP3A4 in the metabolism of paliperidone, there is no evidence in vivo that these isozymes play a significant role in the metabolism of paliperidone. Population pharmacokinetics analyses indicated no discernible difference on the apparent clearance of paliperidone after administration of oral paliperidone between extensive metabolizers and poor metabolizers of CYP2D6 substrates.

The median apparent half-life of paliperidone following INVEGA SUSTENNA single-dose administration over the dose range of 39 mg – 234 mg ranged from 25 days – 49 days.

Long-Acting Paliperidone Palmitate Injection versus Oral Extended-Release Paliperidone

INVEGA SUSTENNA is designed to deliver paliperidone over a monthly period while extended-release oral paliperidone is administered on a daily basis. The initiation regimen for INVEGA SUSTENNA (234 mg/156 mg in the deltoid muscle on Day 1/Day 8) was designed to rapidly attain steady-state paliperidone concentrations when initiating therapy without the use of oral supplementation.

In general, overall initiation plasma levels with INVEGA SUSTENNA were within the exposure range observed with 6–12 mg extended-release oral paliperidone. The use of the INVEGA SUSTENNA initiation regimen allowed patients to stay in this exposure window of 6–12 mg extended-release oral paliperidone even on trough pre-dose days (Day 8 and Day 36). The intersubject variability for paliperidone pharmacokinetics following delivery from INVEGA SUSTENNA was lower relative to the variability determined from extended-release oral paliperidone tablets. Because of the difference in median pharmacokinetic profiles between the two products, caution should be exercised when making a direct comparison of their pharmacokinetic properties.

Drug Interaction Studies

No specific drug interaction studies have been performed with INVEGA SUSTENNA. The information below is obtained from studies with oral paliperidone.

Effects of other drugs on the exposures of paliperidone are summarized in Figure 1. After oral administration of 20 mg/day of paroxetine (a potent CYP2D6 inhibitor), an increase in mean Cmax and AUC values at steady-state was observed (see Figure 1). Higher doses of paroxetine have not been studied. The clinical relevance is unknown. After oral administration, a decrease in mean Cmax and AUC values at steady state is expected when patients are treated with carbamazepine, a strong inducer of both CYP3A4 and P-gp [see Drug Interactions (7.1)] . This decrease is caused, to a substantial degree, by a 35% increase in renal clearance of paliperidone.

Figure 1: The effects of other drugs on paliperidone pharmacokinetics.

Clinically meaningful pharmacokinetic interaction between INVEGA SUSTENNA and valproate (including valproic acid and divalproex sodium) is not expected. Oral administration of divalproex sodium extended-release tablets (two 500 mg tablets once daily at steady-state) with oral paliperidone extended-release tablets resulted in an increase of approximately 50% in the Cmax and AUC of paliperidone.

After oral administration of paliperidone, the steady-state Cmax and AUC of divalproex sodium extended-release tablets were not affected in 13 patients stabilized on divalproex sodium extended-release tablets. In a clinical study, subjects on stable doses of divalproex sodium extended-release tablets had comparable valproate average plasma concentrations when oral paliperidone extended-release tablets 3–15 mg/day was added to their existing divalproex sodium extended-release tablets treatment [see Drug Interactions (7.2)] .

In vitro studies indicate that CYP2D6 and CYP3A4 may be involved in paliperidone metabolism, however, there is no evidence in vivo that inhibitors of these enzymes significantly affect the metabolism of paliperidone; they contribute to only a small fraction of total body clearance. In vitro studies demonstrated that paliperidone is a substrate of P-glycoprotein (P-gp) [see Drug Interactions (7.2)] .

In vitro studies in human liver microsomes demonstrated that paliperidone does not substantially inhibit the metabolism of drugs metabolized by cytochrome P450 isozymes, including CYP1A2, CYP2A6, CYP2C8/9/10, CYP2D6, CYP2E1, CYP3A4, and CYP3A5. Therefore, paliperidone is not expected to inhibit clearance of drugs that are metabolized by these metabolic pathways in a clinically relevant manner. Paliperidone is also not expected to have enzyme inducing properties.

Paliperidone is a weak inhibitor of P-gp at high concentrations. No in vivo data are available, and the clinical relevance is unknown.

Studies in Specific Populations

No specific pharmacokinetic studies have been performed with INVEGA SUSTENNA in specific populations. All the information is obtained from studies with oral paliperidone or is based on the population pharmacokinetic modelling of oral paliperidone and INVEGA SUSTENNA. Exposures of paliperidone in specific populations (renal impairment, hepatic impairment and elderly) are summarized in Figure 2 [see Dosage and Administration (2.5) and Use in Specific Populations (8.6)] .

After oral administration of paliperidone in patients with moderate hepatic impairment, the plasma concentrations of free paliperidone were similar to those of healthy subjects, although total paliperidone exposure decreased because of a decrease in protein binding. Paliperidone has not been studied in patients with severe hepatic impairment [see Use in Specific Populations (8.7)] .

After oral administration of paliperidone in elderly subjects, the Cmax and AUC increased 1.2-fold compared to young subjects. However, there may be age-related decreases in creatinine clearance [see Dosage and Administration (2.5) and Use in Specific Populations (8.5)] .

Figure 2: Effects of intrinsic factors on paliperidone pharmacokinetics.

Based on in vitro studies utilizing human liver enzymes, paliperidone is not a substrate for CYP1A2; smoking should, therefore, not have an effect on the pharmacokinetics of paliperidone.

Slower absorption was observed in females in a population pharmacokinetic analysis. At apparent steady-state with INVEGA SUSTENNA, the trough concentrations were similar between males and females.

Lower Cmax was observed in overweight and obese subjects. At apparent steady-state with INVEGA SUSTENNA, the trough concentrations were similar among normal, overweight, and obese subjects.

13 NONCLINICAL TOXICOLOGY

13.1 Carcinogenesis, Mutagenesis, Impairment of Fertility

Carcinogenesis

The carcinogenic potential of intramuscularly injected paliperidone palmitate was assessed in rats. There was an increase in mammary gland adenocarcinomas in female rats at 16, 47, and 94 mg/kg/month, which is 0.6, 2, and 4 times, respectively, the MRHD of 234 mg of INVEGA SUSTENNA based on mg/m^2 body surface area. A no-effect dose was not established. Male rats showed an increase in mammary gland adenomas, fibroadenomas, and carcinomas at 2 and 4 times the MRHD based on mg/m^2body surface area. A carcinogenicity study in mice has not been conducted with paliperidone palmitate.

Carcinogenicity studies with risperidone, which is extensively converted to paliperidone in rats, mice, and humans, were conducted in Swiss albino mice and Wistar rats. Risperidone was administered in the diet at daily doses of 0.63, 2.5, and 10 mg/kg for 18 months to mice and for 25 months to rats. A maximum tolerated dose was not achieved in male mice. There were statistically significant increases in pituitary gland adenomas, endocrine pancreas adenomas, and mammary gland adenocarcinomas. The no-effect dose for these tumors was less than or equal to the maximum recommended human dose of risperidone based on mg/m^2 body surface area (see risperidone package insert). An increase in mammary, pituitary, and endocrine pancreas neoplasms has been found in rodents after chronic administration of other antipsychotic drugs and is considered to be mediated by prolonged dopamine D2 antagonism and hyperprolactinemia. The relevance of these tumor findings in rodents to human risk is unclear [see Warnings and Precautions (5.7)] .

Mutagenesis

Paliperidone palmitate showed no genotoxicity in the in vitro Ames bacterial reverse mutation test or the mouse lymphoma assay. Paliperidone was not genotoxic in the in vitro Ames bacterial reverse mutation test, the mouse lymphoma assay, or the in vivo rat bone marrow micronucleus test.

Impairment of Fertility

No fertility studies were conducted with paliperidone palmitate.

In an oral paliperidone study of fertility, the percentage of treated female rats that became pregnant was not affected at oral doses of paliperidone of up to 2.5 mg/kg/day which is 2 times the MRHD based on mg/m^2 body surface area. However, pre- and post-implantation loss was increased, and the number of live embryos was slightly decreased, at 2.5 mg/kg, a dose that also caused slight maternal toxicity. These parameters were not affected at a dose of 0.63 mg/kg, which is half of the MRHD based on mg/m^2 body surface area.

The fertility of male rats was not affected at oral doses of paliperidone of up to 2 times the MRHD of 12 mg/day based on mg/m^2 body surface area, although sperm count and sperm viability studies were not conducted with paliperidone. In a subchronic study in Beagle dogs with risperidone, which is extensively converted to paliperidone in dogs and humans, all doses tested (0.31 mg/kg – 5.0 mg/kg) resulted in decreases in serum testosterone and in sperm motility and concentration (0.6 to 10 times the MRHD of 16 mg/day for risperidone, based on mg/m^2 body surface area). Serum testosterone and sperm parameters partially recovered, but remained decreased after the last observation (two months after treatment was discontinued).

14 CLINICAL STUDIES

14.1 Schizophrenia

Short-Term Monotherapy (Studies 1, 2, 3, 4)

The efficacy of INVEGA SUSTENNA in the acute treatment of schizophrenia was evaluated in four short-term (one 9-week and three 13-week) double-blind, randomized, placebo-controlled, fixed-dose studies of acutely relapsed adult inpatients who met DSM-IV criteria for schizophrenia. The fixed doses of INVEGA SUSTENNA in these studies were given on days 1, 8, and 36 in the 9-week study, and additionally on day 64 of the 13-week studies, i.e., at a weekly interval for the initial two doses and then every 4 weeks for maintenance.

Efficacy was evaluated using the total score on the Positive and Negative Syndrome Scale (PANSS). The PANSS is a 30-item scale that measures positive symptoms of schizophrenia (7 items), negative symptoms of schizophrenia (7 items), and general psychopathology (16 items), each rated on a scale of 1 (absent) to 7 (extreme); total PANSS scores range from 30 to 210.

In Study 1 (PSY-3007), a 13-week study (n=636) comparing three fixed doses of INVEGA SUSTENNA (initial deltoid injection of 234 mg followed by 3 gluteal or deltoid doses of either 39 mg/4 weeks, 156 mg/4 weeks or 234 mg/4 weeks) to placebo, all three doses of INVEGA SUSTENNA were superior to placebo in improving the PANSS total score.

In Study 2 (PSY-3003), another 13-week study (n=349) comparing three fixed doses of INVEGA SUSTENNA (78 mg/4 weeks, 156 mg/4 weeks, and 234 mg/4 weeks) to placebo, only 156 mg/4 weeks of INVEGA SUSTENNA was superior to placebo in improving the PANSS total score.

In Study 3 (PSY-3004), a third 13-week study (n=513) comparing three fixed doses of INVEGA SUSTENNA (39 mg/4 weeks, 78 mg/4 weeks, and 156 mg/4 weeks) to placebo, all three doses of INVEGA SUSTENNA were superior to placebo in improving the PANSS total score.

In Study 4 (SCH-201), the 9-week study (n=197) comparing two fixed doses of INVEGA SUSTENNA (78 mg/4 weeks and 156 mg/4 weeks) to placebo, both doses of INVEGA SUSTENNA were superior to placebo in improving PANSS total score.

A summary of the mean baseline PANSS scores along with the mean changes from baseline in the four short-term acute schizophrenia studies are provided in Table 14.

Table 14: Schizophrenia Short-term Studies
Study Number | Treatment Group | Primary Efficacy Measure: PANSS Total Score
 |  | Mean Baseline Score (SD) | LS Mean Change from Baseline (SE) | Placebo-subtracted Difference [Difference (drug minus placebo) in least-squares mean change from baseline.] (95% CI)
Study 1 | INVEGA SUSTENNA (39 mg/4 weeks) [p<0.05 (Doses statistically significantly superior to placebo).] | 86.9 (11.99) | -11.2 (1.69) | -5.1 (-9.01, -1.10)
Study 1 | INVEGA SUSTENNA (156 mg/4 weeks) | 86.2 (10.77) | -14.8 (1.68) | -8.7 (-12.62, -4.78)
Study 1 | INVEGA SUSTENNA (234 mg/4 weeks) | 88.4 (11.70) | -15.9 (1.70) | -9.8 (-13.71, -5.85)
Study 1 | Placebo | 86.8 (10.31) | -6.1 (1.69) | --
Study 2 [Because an insufficient number of subjects received the 234 mg/4 weeks dose, results from this group are not included.] | INVEGA SUSTENNA (78 mg/4 weeks) | 89.9 (10.78) | -6.9 (2.50) | -3.5 (-8.73, 1.77)
Study 2 [Because an insufficient number of subjects received the 234 mg/4 weeks dose, results from this group are not included.] | INVEGA SUSTENNA (156 mg/4 weeks) | 90.1 (11.66) | -10.4 (2.47) | -6.9 (-12.12, -1.68)
Study 2 [Because an insufficient number of subjects received the 234 mg/4 weeks dose, results from this group are not included.] | Placebo | 92.4 (12.55) | -3.5 (2.15) | --
Study 3 | INVEGA SUSTENNA (39 mg/4 weeks) | 90.7 (12.25) | -19.8 (2.19) | -6.6 (-11.40, -1.73)
Study 3 | INVEGA SUSTENNA (78 mg/4 weeks) | 91.2 (12.02) | -19.2 (2.19) | -5.9 (-10.76, -1.07)
Study 3 | INVEGA SUSTENNA (156 mg/4 weeks) | 90.8 (11.70) | -22.5 (2.18) | -9.2 (-14.07, -4.43)
Study 3 | Placebo | 90.7 (12.22) | -13.3 (2.21) | --
Study 4 | INVEGA SUSTENNA (78 mg/4 weeks) | 88.0 (12.39) | -4.6 (2.43) | -11.2 (-16.85, -5.57)
Study 4 | INVEGA SUSTENNA (156 mg/4 weeks) | 85.2 (11.09) | -7.4 (2.45) | -14.0 (-19.51, -8.58)
Study 4 | Placebo | 87.8 (13.90) | 6.6 (2.45) | --
SD: standard deviation; SE: standard error; LS Mean: least-squares mean; CI: unadjusted confidence interval.

Maintenance Monotherapy Treatment (Study 5: PSY-3001)

The efficacy of INVEGA SUSTENNA in maintaining symptomatic control in schizophrenia was established in a longer-term double-blind, placebo-controlled, flexible-dose study involving adult subjects who met DSM-IV criteria for schizophrenia. This study included a minimum 12-week, fixed-dose stabilization phase, and a randomized, placebo-controlled phase to observe for relapse. During the double-blind phase, patients were randomized to either the same dose of INVEGA SUSTENNA they received during the stabilization phase, i.e., 39 mg, 78 mg, or 156 mg administered every 4 weeks, or to placebo. A total of 410 stabilized patients were randomized to either INVEGA SUSTENNA or to placebo until they experienced a relapse of schizophrenia symptoms. Relapse was pre-defined as time to first emergence of one or more of the following: psychiatric hospitalization, ≥ 25% increase (if the baseline score was > 40) or a 10-point increase (if the baseline score was ≤ 40) in total PANSS score on two consecutive assessments, deliberate self-injury, violent behavior, suicidal/homicidal ideation, or a score of ≥ 5 (if the maximum baseline score was ≤ 3) or ≥ 6 (if the maximum baseline score was 4) on two consecutive assessments of the specific PANSS items. The primary efficacy variable was time to relapse. A pre-planned interim analysis showed a statistically significantly longer time to relapse in patients treated with INVEGA SUSTENNA compared to placebo, and the study was stopped early because maintenance of efficacy was demonstrated. Thirty-four percent (34%) of subjects in the placebo group and 10% of subjects in the INVEGA SUSTENNA group experienced a relapse event. There was a statistically significant difference between the treatment groups in favor of INVEGA SUSTENNA. A Kaplan-Meier plot of time to relapse by treatment group is shown in Figure 3. The time to relapse for subjects in the placebo group was statistically significantly shorter than for the INVEGA SUSTENNA group. An examination of population subgroups did not reveal any clinically significant differences in responsiveness on the basis of gender, age, or race.

Figure 3: Kaplan-Meier Plot of Cumulative Proportion of Subjects with Relapse Over Time (Schizophrenia Study 5)

Long-Term Comparative Monotherapy Treatment versus Oral Antipsychotic Therapy (Study 6: SCH-3006)

The efficacy of INVEGA SUSTENNA in delaying time to treatment failure compared with selected oral antipsychotic medications was established in a long-term, randomized, flexible-dose study in subjects with schizophrenia and a history of incarceration. Subjects were screened for up to 14 days followed by a 15-month treatment phase during which they were observed for treatment failure.

The primary endpoint was time to first treatment failure. Treatment failure was defined as one of the following: arrest and/or incarceration; psychiatric hospitalization; discontinuation of antipsychotic treatment because of safety or tolerability; treatment supplementation with another antipsychotic because of inadequate efficacy; need for increase in level of psychiatric services to prevent an imminent psychiatric hospitalization; discontinuation of antipsychotic treatment because of inadequate efficacy; or suicide. Treatment failure was determined by an Event Monitoring Board (EMB) that was blinded to treatment assignment. A total of 444 subjects were randomly assigned to either INVEGA SUSTENNA (N = 226; median dose 156 mg) or one of up to seven pre-specified, flexibly-dosed, commonly prescribed oral antipsychotic medications (N = 218; aripiprazole, haloperidol, olanzapine, paliperidone, perphenazine, quetiapine, or risperidone). The selection of the oral antipsychotic medication was determined to be appropriate for the patient by the investigator. A statistically significantly longer time to first treatment failure was seen for INVEGA SUSTENNA compared with oral antipsychotic medications. The median time to treatment failure was 416 days and 226 days for INVEGA SUSTENNA and antipsychotic medications, respectively. A Kaplan-Meier plot of time to first treatment failure is shown in Figure 4. The frequencies of first treatment failure events by type are shown in Table 15. The time to first arrest and/or incarceration or psychiatric hospitalization was also statistically significantly longer for the INVEGA SUSTENNA group compared to the oral antipsychotic group.

Figure 4: Kaplan-Meier Plot of Time to First Treatment Failure in a Long-Term, Randomized, Flexible-Dose Study in Subjects with Schizophrenia and a History of Incarceration (Schizophrenia Study 6)

*Median time to first treatment failure: 416 days with INVEGA SUSTENNA; 226 days with oral antipsychotics

Table 15: Components of Composite Endpoint in a Long-Term, Randomized, Flexible-Dose Study in Subjects with Schizophrenia and a History of Incarceration (Schizophrenia Study 6)
Event Type | INVEGA SUSTENNA N=226 frequency (%) | Oral Antipsychotics N=218 frequency (%) | Hazard Ratio [Hazard ratio of INVEGA SUSTENNA to Oral Antipsychotics based on Cox regression model for time-to-event analysis. Note that the hazard ratio did not appear constant throughout the trial.] [95% CI]
First Treatment Failures | 90 (39.8%) | 117 (53.7%) | 0.70 [0.53, 0.92]
First Treatment Failure Component Events
- Arrest and/or incarceration | 48 (21.2%) | 64 (29.4%)
- Psychiatric hospitalization | 18 (8.0%) | 26 (11.9%)
- Discontinuation of antipsychotic treatment because of safety or tolerability | 15 (6.6%) | 8 (3.7%)
- Treatment supplementation with another antipsychotic because of inadequate efficacy | 5 (2.2%) | 6 (2.8%)
- Need for increase in level of psychiatric services to prevent an imminent psychiatric hospitalization | 3 (1.3%) | 4 (1.8%)
- Discontinuation of antipsychotic treatment because of inadequate efficacy | 1 (0.4%) | 9 (4.1%)
- Suicide | 0 | 0
Arrest and/or Incarceration or Psychiatric Hospitalization Events, regardless of whether they were first events [Analysis results, which incorporated relevant events collected after discontinuation for those who discontinued, were consistent with the results from the pre-specified analysis of this secondary endpoint.] | 76 (33.6%) | 98 (45.0%) | 0.70 [0.52, 0.94]

14.2 Schizoaffective Disorder

Maintenance Treatment – Monotherapy and as Adjunct to Mood Stabilizer or Antidepressant (SAff Study 1: SCA-3004)

The efficacy of INVEGA SUSTENNA in maintaining symptom control in schizoaffective disorder was established in a long-term double-blind, placebo-controlled, flexible-dose randomized-withdrawal study designed to delay relapse in adult subjects who met DSM-IV criteria for schizoaffective disorder, as confirmed by the Structured Clinical Interview for DSM-IV Disorders. The population included subjects with schizoaffective bipolar and depressive types. Subjects received INVEGA SUSTENNA either as monotherapy or as an adjunct to stable doses of antidepressant or mood stabilizers.

This study included a 13-week, open-label, flexible-dose (INVEGA SUSTENNA 78 mg, 117 mg, 156 mg, or 234 mg) lead-in period which enrolled a total of 667 subjects who had 1) acute exacerbation of psychotic symptoms; 2) score ≥4 on ≥3 PANSS items of delusions, conceptual disorganization, hallucinatory behavior, excitement, suspiciousness/persecution, hostility, uncooperativeness, tension, and poor impulse control; and 3) prominent mood symptoms ≥16 on the Young Mania Rating Scale (YMRS) and/or the Hamilton Rating Scale for Depression, 21-item version (HAM-D-21). Subjects were 19 to 66 years old (mean 39.5 years) and 53.5% were male. The mean scores at open-label enrollment of PANSS total was 85.8 (range 42 to 128), HAM-D-21 was 20.4 (range 3 to 43), YMRS was 18.6 (range 0 to 50), and CGI-S-SCA was 4.4 (range 2 to 6).

After the 13-week open-label flexible-dose INVEGA SUSTENNA treatment, 432 subjects met stabilization criteria (PANSS total score ≤70, YMRS ≤12, and HAM-D-21 ≤12) and continued into the 12-week open-label fixed-dose stabilization period.

A total of 334 subjects who met stabilization criteria for 12 consecutive weeks were randomized (1:1) to continue the same dose of INVEGA SUSTENNA or to placebo in the 15-month, double-blind, maintenance period. For the 164 subjects who were randomized to INVEGA SUSTENNA, dose distribution was 78 mg (4.9%), 117 mg (9.8%), 156 mg (47.0%), and 234 mg (38.4%). The primary efficacy variable was time to relapse. Relapse was defined as the first occurrence of one or more of the following: 1) psychiatric hospitalization; 2) intervention employed to avert hospitalization; 3) clinically significant self-injury, suicidal or homicidal ideation or violent behavior; 4) a score of ≥6 (if the score was ≤4 at randomization) of any of the individual PANSS items: delusions, conceptual disorganization, hallucinatory behavior, excitement, suspiciousness/persecution, hostility, uncooperativeness, or poor impulse control; 5) on two consecutive assessments within 7 days: ≥25% increase (if the score at randomization was >45) or ≥10-point increase (if the score at randomization was ≤45) in total PANSS score; a score of ≥5 (if the score was ≤3 at randomization) of any of the individual PANSS items: delusions, conceptual disorganization, hallucinatory behavior, excitement, suspiciousness/persecution, hostility, uncooperativeness, or poor impulse control; an increase of ≥2 points (if the score was 1 [not ill] to 3 [mildly ill] at randomization) or increase of ≥1 point (if the score was ≥4 [moderately ill or worse] at randomization) in CGI-S-SCA overall score.

There was a statistically significant difference in time to relapse between the treatment groups in favor of INVEGA SUSTENNA. A Kaplan-Meier plot of time to relapse by treatment group is shown in Figure 5.

Figure 5: Kaplan-Meier Plot of Cumulative Proportion of Subjects with Relapse Over Time (SAff Study 1)

Table 16 summarizes the number of subjects with relapse in the overall population, by subgroup (monotherapy vs. adjunctive therapy), and by symptom type at the first occurrence of relapse.

Table 16: Summary of Relapse Rates (SAff Study 1).
 | Number (Percent) of Subjects Who Relapsed
 | Placebo N=170 | INVEGA SUSTENNA N=164
All Subjects | 57 (33.5%) | 25 (15.2%)
Monotherapy subset | N=73 24 (32.9%) | N=78 9 (11.5%)
Adjunct to Antidepressants or Mood Stabilizer subset | N=97 33 (34.0%) | N=86 16 (18.6%)
Psychotic Symptoms [8 subjects experienced a relapse without psychotic symptoms.] | 53 (31.2%) | 21 (12.8%)
Mood Symptoms [16 subjects experienced a relapse without any mood symptoms.]
Any Mood Symptoms | 48 (28.2%) | 18 (11.0%)
Manic | 16 (9.4%) | 5 (3.0%)
Depressive | 23 (13.5%) | 8 (4.9%)
Mixed | 9 (5.3%) | 5 (3.0%)

16 HOW SUPPLIED/STORAGE AND HANDLING

INVEGA SUSTENNA® is available as a white to off-white sterile aqueous extended-release suspension for intramuscular injection in dose strengths of 39 mg/0.25 mL, 78 mg/0.5 mL, 117 mg/0.75 mL, 156 mg/mL, and 234 mg/1.5 mL paliperidone palmitate in single-dose prefilled syringes. The single-use kit contains a prefilled syringe and 2 safety needles (a 1 ½-inch 22 gauge safety needle and a 1-inch 23 gauge safety needle).

39 mg paliperidone palmitate kit | (NDC 50458-560-01)
78 mg paliperidone palmitate kit | (NDC 50458-561-01)
117 mg paliperidone palmitate kit | (NDC 50458-562-01)
156 mg paliperidone palmitate kit | (NDC 50458-563-01)
234 mg paliperidone palmitate kit | (NDC 50458-564-01)

Storage and Handling

Store at room temperature (25 °C, 77 °F); excursions between 15 °C and 30 °C (between 59 °F and 86 °F) are permitted. Do not mix with any other product or diluent.

17 PATIENT COUNSELING INFORMATION

Advise the patient to read the FDA-approved patient labeling (Patient Information).

Neuroleptic Malignant Syndrome (NMS)

Counsel patients about a potentially fatal adverse reaction, Neuroleptic Malignant Syndrome (NMS), that has been reported in association with administration of antipsychotic drugs. Advise patients, family members, or caregivers to contact their healthcare provider or report to the emergency room if they experience signs and symptoms of NMS, including hyperpyrexia, muscle rigidity, altered mental status including delirium, and evidence of autonomic instability (irregular pulse or blood pressure, tachycardia, diaphoresis, and cardiac dysrhythmia) [see Warnings and Precautions (5.3)].

Tardive Dyskinesia

Counsel patients on the signs and symptoms of tardive dyskinesia and to contact their healthcare provider if these abnormal movements occur [see Warnings and Precautions (5.5)].

Metabolic Changes

Educate patients about the risk of metabolic changes, how to recognize symptoms of hyperglycemia and diabetes mellitus, and the need for specific monitoring, including blood glucose, lipids, and weight [see Warnings and Precautions (5.6)].

Orthostatic Hypotension

Educate patients about the risk of orthostatic hypotension and syncope, particularly at the time of initiating treatment, re-initiating treatment, or increasing the dose [see Warnings and Precautions (5.7)] .

Leukopenia/Neutropenia

Advise patients with a pre-existing low WBC or a history of drug-induced leukopenia/neutropenia that they should have their CBC monitored while taking INVEGA SUSTENNA [see Warnings and Precautions (5.9)] .

Hyperprolactinemia

Counsel patients on signs and symptoms of hyperprolactinemia that may be associated with chronic use of INVEGA SUSTENNA. Advise them to seek medical attention if they experience any of the following: amenorrhea or galactorrhea in females, erectile dysfunction or gynecomastia in males [see Warnings and Precautions (5.10)] .

Interference with Cognitive and Motor Performance

Caution patients about performing activities requiring mental alertness, such as operating hazardous machinery or operating a motor vehicle, until they are reasonably certain that INVEGA SUSTENNA therapy does not affect them adversely [see Warnings and Precautions (5.11)] .

Priapism

Advise patients of the possibility of painful or prolonged penile erections (priapism). Instruct the patient to seek immediate medical attention in the event of priapism [see Warnings and Precautions (5.14)] .

Heat Exposure and Dehydration

Counsel patients regarding appropriate care in avoiding overheating and dehydration [see Warnings and Precautions (5.15)] .

Concomitant Medication

Advise patients to inform their healthcare providers if they are taking, or plan to take any prescription or over-the-counter medications because there is a potential for clinically significant interactions [see Drug Interactions (7)] .

Alcohol

Advise patients to avoid alcohol during treatment with INVEGA SUSTENNA [see Drug Interactions (7.1)] .

Pregnancy

Advise patients to notify their healthcare provider if they become pregnant or intend to become pregnant during treatment with INVEGA SUSTENNA. Advise patients that INVEGA SUSTENNA may cause extrapyramidal and/or withdrawal symptoms in a neonate. Advise patients that there is a pregnancy registry that monitors pregnancy outcomes in women exposed to INVEGA SUSTENNA during pregnancy [see Use in Specific Populations (8.1)] .

Lactation

Advise breastfeeding women using INVEGA SUSTENNA to monitor infants for somnolence, failure to thrive, jitteriness, and extrapyramidal symptoms (tremors and abnormal muscle movements) and to seek medical care if they notice these signs [see Use in Specific Populations (8.2)] .

Infertility

Advise females of reproductive potential that INVEGA SUSTENNA may impair fertility due to an increase in serum prolactin levels. The effects on fertility are reversible [see Use in Specific Populations (8.3)].

INVEGA SUSTENNA (paliperidone palmitate) Extended-Release Injectable Suspension

Manufactured for:
Janssen Pharmaceuticals, Inc.
Titusville, NJ 08560, USA

For patent information: www.janssenpatents.com

© Johnson & Johnson and its affiliates 2009

PATIENT INFORMATION
INVEGA SUSTENNA® (in-VAY-guh suss-TEN-uh)
(paliperidone palmitate)
Extended-Release Injectable Suspension

What is the most important information I should know about INVEGA SUSTENNA?

INVEGA SUSTENNA can cause serious side effects, including:

- Increased risk of death in elderly people who are confused, have memory loss and have lost touch with reality (dementia-related psychosis). INVEGA SUSTENNA is not for treating dementia-related psychosis.

What is INVEGA SUSTENNA?

INVEGA SUSTENNA is a prescription medicine given by injection by a healthcare professional and used to treat:

- schizophrenia in adults
- schizoaffective disorder in adults either alone or with other medicines such as mood stabilizers or antidepressants

It is not known if INVEGA SUSTENNA is safe and effective in children under 18 years of age.

Who should not receive INVEGA SUSTENNA?

Do not receive INVEGA SUSTENNA if you:

- are allergic to paliperidone, paliperidone palmitate, risperidone, or any of the ingredients in INVEGA SUSTENNA. See the end of this Patient Information leaflet for a complete list of ingredients in INVEGA SUSTENNA.

What should I tell my healthcare provider before receiving INVEGA SUSTENNA?

Before you receive INVEGA SUSTENNA, tell your healthcare provider about all your medical conditions, including if you:

- have had Neuroleptic Malignant Syndrome (NMS)
- have or have had heart problems, including a heart attack, heart failure, abnormal heart rhythm, or long QT syndrome
- have or have had low levels of potassium or magnesium in your blood
- have or have had uncontrolled movements of your tongue, face, mouth, or jaw (tardive dyskinesia)
- have or have had kidney or liver problems
- have diabetes or have a family history of diabetes
- have had a low white blood cell count
- have had problems with dizziness or fainting or are being treated for high blood pressure
- have or have had seizures or epilepsy
- have any other medical conditions
- are pregnant or plan to become pregnant. It is not known if INVEGA SUSTENNA will harm your unborn baby.
  - If you become pregnant while taking INVEGA SUSTENNA, talk to your healthcare provider about registering with the National Pregnancy Registry for Atypical Antipsychotics. You can register by calling 1-866-961-2388 or visit http://womensmentalhealth.org/clinical-and-research-programs/pregnancyregistry/.
  - Infants born to women who are treated with INVEGA SUSTENNA may experience symptoms such as tremors, irritability, excessive sleepiness, eye twitching, muscle spasms, decreased appetite, difficulty breathing, or abnormal movement of arms and legs. Let your healthcare provider know if these symptoms occur.
- are breastfeeding or plan to breastfeed. INVEGA SUSTENNA can pass into your breast milk. Talk to your healthcare provider about the best way to feed your baby if you receive INVEGA SUSTENNA.

Tell your healthcare provider about all the medicines you take, including prescription and over-the-counter medicines, vitamins, and herbal supplements.

Know the medicines you take. Keep a list of them to show to your healthcare provider or pharmacist when you get a new medicine.

How will I receive INVEGA SUSTENNA?

- Follow your INVEGA SUSTENNA treatment schedule exactly as your healthcare provider tells you to.
- Your healthcare provider will tell you how much INVEGA SUSTENNA you will receive and when you will receive it.
- INVEGA SUSTENNA is given as an injection by your healthcare provider into the muscle (intramuscularly) of your arm or your buttocks.
- When you receive your first dose of INVEGA SUSTENNA you will need to get a second dose 1 week later. After that you will only need to get a dose 1 time a month.

What should I avoid while receiving INVEGA SUSTENNA?

- INVEGA SUSTENNA may affect your ability to make decisions, think clearly, or react quickly. Do not drive, operate heavy machinery, or do other dangerous activities until you know how INVEGA SUSTENNA affects you.
- Avoid getting overheated or dehydrated.

What are the possible side effects of INVEGA SUSTENNA?

INVEGA SUSTENNA may cause serious side effects, including:

- See " What is the most important information I should know about INVEGA SUSTENNA"
- stroke in elderly people (cerebrovascular problems) that can lead to death
- Neuroleptic Malignant Syndrome (NMS). NMS is a rare but very serious problem that can happen in people who receive INVEGA SUSTENNA. NMS can cause death and must be treated in a hospital. Call your healthcare provider right away if you become severely ill and have any of these symptoms:
  - high fever
  - severe muscle stiffness
  - confusion
  - loss of consciousness
  - changes in your breathing, heartbeat and blood pressure
- problems with your heartbeat. These heart problems can cause death. Call your healthcare provider right away if you have any of these symptoms:
  - passing out or feeling like you will pass out
  - dizziness
  - feeling as if your heart is pounding or missing beats
- uncontrolled movements of your tongue, face, mouth, or jaw (tardive dyskinesia)
- metabolic changes. Metabolic changes may include high blood sugar (hyperglycemia), diabetes mellitus and changes in the fat levels in your blood (dyslipidemia), and weight gain.
- low blood pressure and fainting
- changes in your blood cell counts
- high level of prolactin in your blood (hyperprolactinemia). INVEGA SUSTENNA may cause a rise in the blood levels of a hormone called prolactin (hyperprolactinemia) that may cause side effects including missed menstrual periods, leakage of milk from the breasts, development of breasts in men, or problems with erection.
- problems thinking clearly and moving your body
- seizures
- difficulty swallowing that can cause food or liquid to get into your lungs
- prolonged or painful erection lasting more than 4 hours. Call your healthcare provider or go to your nearest emergency room right away if you have an erection that lasts more than 4 hours.
- problems with control of your body temperature especially when you exercise a lot or spend time doing things that make you warm. It is important for you to drink water to avoid dehydration.

The most common side effects of INVEGA SUSTENNA include: injection site reactions, sleepiness or drowsiness, dizziness, feeling restlessness or needing to be constantly moving, abnormal muscle movements including tremor (shaking), shuffling, uncontrolled involuntary movements, and abnormal movements of your eyes.

Tell your healthcare provider if you have any side effect that bothers you or does not go away.

These are not all the possible side effects of INVEGA SUSTENNA. For more information, ask your healthcare provider or pharmacist.

Call your doctor for medical advice about side effects. You may report side effects to FDA at 1-800-FDA-1088.

General information about the safe and effective use of INVEGA SUSTENNA.

Medicines are sometimes prescribed for purposes other than those listed in a Patient Information leaflet. Do not use INVEGA SUSTENNA for a condition for which it was not prescribed. Do not give INVEGA SUSTENNA to other people, even if they have the same symptoms that you have. It may harm them. You can ask your pharmacist or healthcare provider for information about INVEGA SUSTENNA that is written for healthcare professionals.

This Patient Information leaflet summarizes the most important information about INVEGA SUSTENNA. If you would like more information, talk with your healthcare provider.

You can ask your healthcare provider or pharmacist for more information that is written for healthcare professionals. For more information, go to www.invegasustenna.com or call 1-800-526-7736.

What are the ingredients in INVEGA SUSTENNA?

Active ingredient: paliperidone palmitate

Inactive ingredients: polysorbate 20, polyethylene glycol 4000, citric acid monohydrate, sodium dihydrogen phosphate monohydrate, sodium hydroxide, and water for injection

Manufactured for: Janssen Pharmaceuticals, Inc., Titusville, NJ 08560, USA
For patent information: www.janssenpatents.com
© Johnson & Johnson and its affiliates 2009

This Patient Information has been approved by the U.S. Food and Drug Administration. Revised: January 2025

INSTRUCTIONS FOR USE

INVEGA SUSTENNA®

(paliperidone palmitate)
extended-release injectable suspension

Rx only

Single use only

PLEASE READ COMPLETE INSTRUCTIONS PRIOR TO USE

For deltoid and gluteal intramuscular injection only

Please see accompanying full Package Insert.

IMPORTANT RESOURCES

For additional information, visit www.invegasustenna.com or call Janssen Pharmaceuticals, Inc. at 1-800-526-7736.

Kit contents

Each injection must be administered only by a health care professional. The kit contains a prefilled syringe and 2 safety needles (a 1 ½-inch 22 gauge needle and a 1-inch 23 gauge needle) for intramuscular injection. INVEGA SUSTENNA is for single use only.

INVEGA SUSTENNA is intended for intramuscular use only. Inject slowly, deep into the muscle. Care should be taken to avoid inadvertent injection into a blood vessel. Each injection should be administered by a health care professional. Administration should be in a single injection. Do not administer the dose in divided injections. Do not administer intravascularly or subcutaneously.

INSTRUCTIONS FOR USE

- Shake the syringe vigorously for a minimum of 10 seconds to ensure a homogeneous suspension.
- Select the appropriate needle.
  For DELTOID injection:
  - If the patient weighs less than 90 kg, use the 1-inch 23 gauge needle (needle with blue colored hub).
  - If the patient weighs 90 kg or more, use the 1 ½-inch 22 gauge needle (needle with gray colored hub).
  For GLUTEAL injection:
  Use the 1 ½-inch 22 gauge needle (needle with gray colored hub) regardless of patient's weight.
- Hold the syringe with the tip cap pointing up. Remove the rubber tip cap with a gentle twisting motion.
- Peel the safety needle pouch half way open. Grasp the needle sheath using the plastic peel pouch. Hold the syringe pointing up. Attach the safety needle to the syringe using a gentle twisting motion to avoid needle hub cracks or damage. Always check for signs of damage or leaking prior to administration.
- Pull the needle sheath away from the needle with a straight pull. Do not twist the sheath as the needle may be loosened from the syringe.
- Bring the syringe with the attached needle in upright position to de-aerate. De-aerate the syringe by moving the plunger rod carefully forward.
- Inject the entire contents intramuscularly slowly, deep into the selected deltoid or gluteal muscle of the patient. Do not administer by any other route.
- After the injection is complete, use either thumb or finger of one hand (h1, h2) or a flat surface (h3) to activate the needle protection system. The needle protection system is fully activated when a 'click' is heard. Discard the syringe with needle appropriately.

Keep out of reach of children.

h1

h2

h3

Manufactured for:
Janssen Pharmaceuticals, Inc.
Titusville, NJ 08560, USA

For patent information: www.janssenpatents.com

© Johnson & Johnson and its affiliates 2009

This Instructions for Use has been approved by the U.S. Food and Drug Administration.

Revised: 2/2025

PRINCIPAL DISPLAY PANEL - 39 mg Syringe Kit

NDC 50458-560-01
Rx only

Single-dose prefilled syringe. Use entire contents of syringe.

INVEGA SUSTENNA®

(paliperidone palmitate)
extended-release injectable suspension
39 mg/0.25 mL

39 mg/0.25 mL
Each single-dose prefilled syringe contains
39 mg (0.25 mL) paliperidone palmitate.

FOR INTRAMUSCULAR INJECTION ONLY
Shake before using

Each injection must be administered only by a healthcare professional.

CONTENTS: 1 single-dose prefilled syringe and 2 needles
(a 22G, 1½-inch safety needle and a 23G, 1-inch safety needle)

Store at room temperature (77°F, 25°C);
excursions between 59°F and 86°F (15°C and 30°C) are permitted.

For initiation and monthly maintenance dosing
instructions, please see accompanying full
Package Insert.

janssen

PRINCIPAL DISPLAY PANEL - 78 mg Syringe Kit

NDC 50458-561-01
Rx only

Single-dose prefilled syringe. Use entire contents of syringe.

INVEGA SUSTENNA®

(paliperidone palmitate)
extended-release injectable suspension
78 mg/0.5 mL

78 mg/0.5 mL
Each single-dose prefilled syringe contains
78 mg (0.5 mL) paliperidone palmitate.

FOR INTRAMUSCULAR INJECTION ONLY
Shake before using

Each injection must be administered only by a healthcare professional.

CONTENTS: 1 single-dose prefilled syringe and 2 needles
(a 22G, 1½-inch safety needle and a 23G, 1-inch safety needle)

Store at room temperature (77°F, 25°C);
excursions between 59°F and 86°F (15°C and 30°C) are permitted.

For initiation and monthly maintenance dosing
instructions, please see accompanying full
Package Insert.

janssen

PRINCIPAL DISPLAY PANEL - 117 mg Syringe Kit

NDC 50458-562-01
Rx only

Single-dose prefilled syringe. Use entire contents of syringe.

INVEGA SUSTENNA®

(paliperidone palmitate)
extended-release injectable suspension
117 mg/0.75 mL

117 mg/0.75 mL
Each single-dose prefilled syringe contains
117 mg (0.75 mL) paliperidone palmitate.

FOR INTRAMUSCULAR INJECTION ONLY
Shake before using

Each injection must be administered only by a healthcare professional.

CONTENTS: 1 single-dose prefilled syringe and 2 needles
(a 22G, 1½-inch safety needle and a 23G, 1-inch safety needle)

Store at room temperature (77°F, 25°C);
excursions between 59°F and 86°F (15°C and 30°C) are permitted.

For initiation and monthly maintenance dosing
instructions, please see accompanying full
Package Insert.

janssen

PRINCIPAL DISPLAY PANEL - 156 mg Syringe Kit

NDC 50458-563-01
Rx only

Single-dose prefilled syringe. Use entire contents of syringe.

INVEGA SUSTENNA®

(paliperidone palmitate)
extended-release injectable suspension
156 mg/mL

156 mg/mL
Each single-dose prefilled syringe contains
156 mg (1 mL) paliperidone palmitate.

FOR INTRAMUSCULAR INJECTION ONLY
Shake before using

Each injection must be administered only by a healthcare professional.

CONTENTS: 1 single-dose prefilled syringe and 2 needles
(a 22G, 1½-inch safety needle and a 23G, 1-inch safety needle)

Store at room temperature (77°F, 25°C);
excursions between 59°F and 86°F (15°C and 30°C) are permitted.

For initiation and monthly maintenance dosing
instructions, please see accompanying full
Package Insert.

janssen

PRINCIPAL DISPLAY PANEL - 234 mg Syringe Kit

NDC 50458-564-01
Rx only

Single-dose prefilled syringe. Use entire contents of syringe.

INVEGA SUSTENNA®

(paliperidone palmitate)
extended-release injectable suspension
234 mg/1.5 mL

234 mg/1.5 mL
Each single-dose prefilled syringe contains
234 mg (1.5 mL) paliperidone palmitate.

FOR INTRAMUSCULAR INJECTION ONLY
Shake before using

Each injection must be administered only by a healthcare professional.

CONTENTS: 1 single-dose prefilled syringe and 2 needles
(a 22G, 1½-inch safety needle and a 23G, 1-inch safety needle)

Store at room temperature (77°F, 25°C);
excursions between 59°F and 86°F (15°C and 30°C) are permitted.

For initiation and monthly maintenance dosing
instructions, please see accompanying full
Package Insert.

janssen